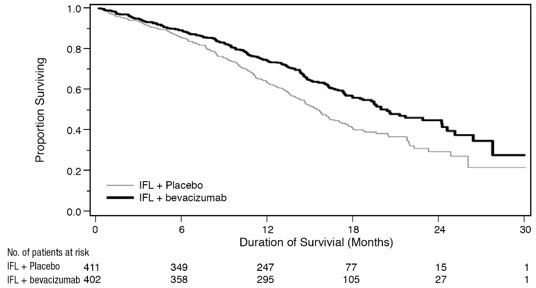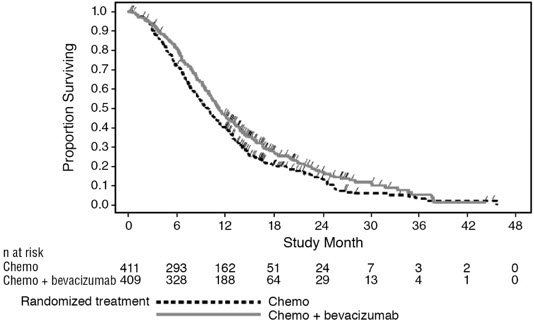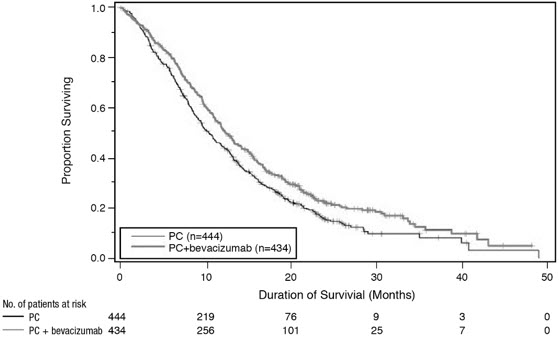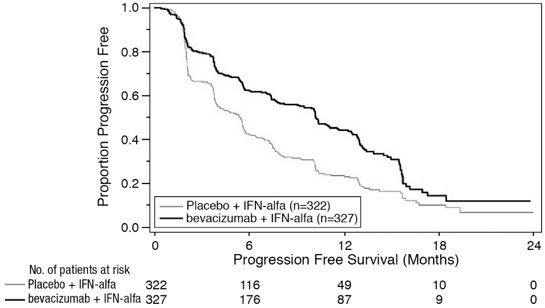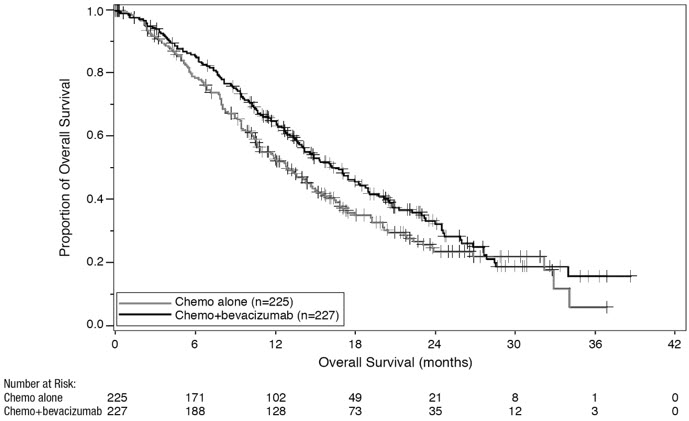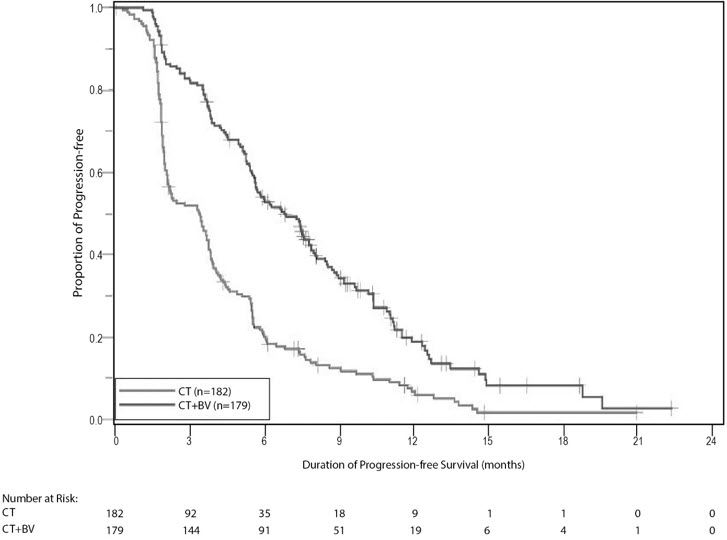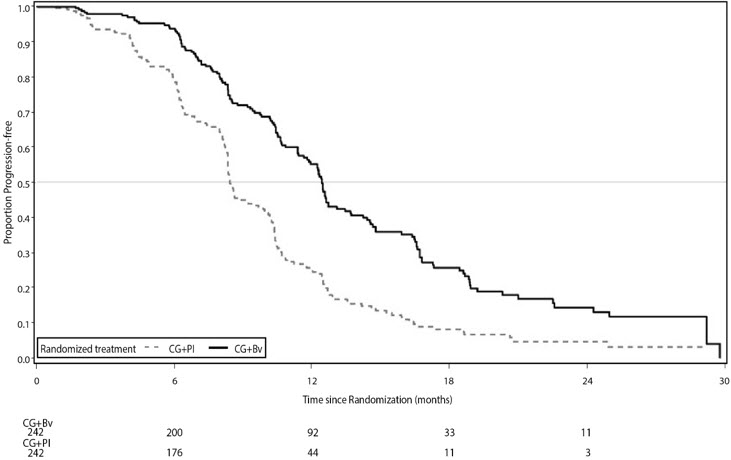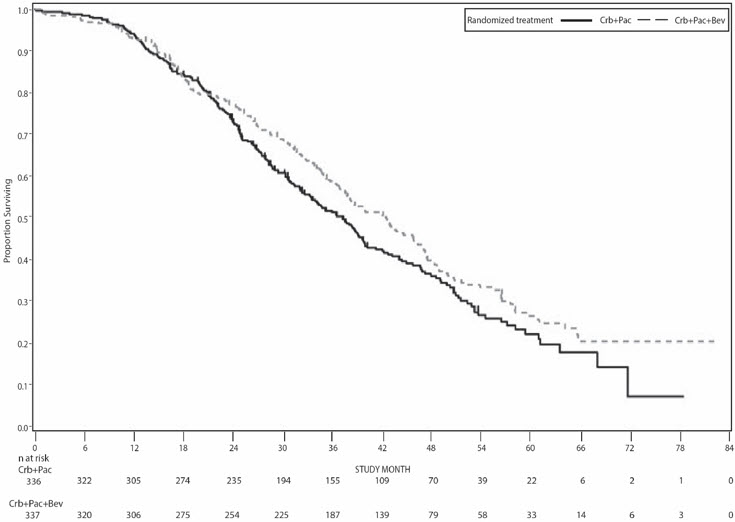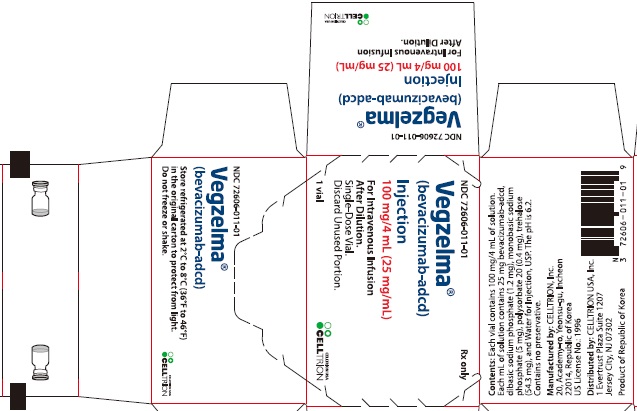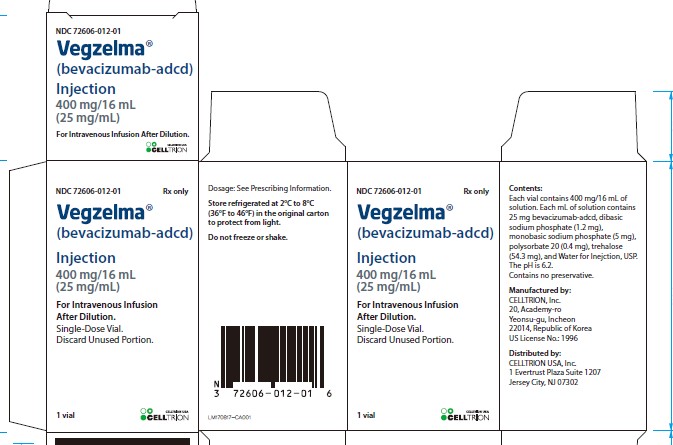 DRUG LABEL: Vegzelma
NDC: 72606-011 | Form: INJECTION, SOLUTION
Manufacturer: CELLTRION USA, Inc.
Category: prescription | Type: HUMAN PRESCRIPTION DRUG LABEL
Date: 20250508

ACTIVE INGREDIENTS: BEVACIZUMAB 100 mg/4 mL
INACTIVE INGREDIENTS: TREHALOSE DIHYDRATE 240 mg/4 mL; SODIUM PHOSPHATE, DIBASIC, ANHYDROUS 4.8 mg/4 mL; POLYSORBATE 20 1.6 mg/4 mL; SODIUM PHOSPHATE, MONOBASIC, MONOHYDRATE 23.2 mg/4 mL; WATER

HIGHLIGHTS OF PRESCRIBING INFORMATION

These highlights do not include all the information needed to use VEGZELMA safely and effectively. See full prescribing information for VEGZELMA.
VEGZELMA (bevacizumab-adcd) injection, for intravenous use
Initial U.S. Approval: 2022
VEGZELMA (bevacizumab-adcd) is biosimilar [Biosimilar means that the biological product is approved based on data demonstrating that it is highly similar to an FDA-approved biological product, known as a reference product, and that there are no clinically meaningful differences between the biosimilar product and the reference product. Biosimilarity of VEGZELMA has been demonstrated for the condition(s) of use (e.g. indication(s), dosing regimen(s)), strength(s), dosage form(s), and route(s) of administration described in its Full Prescribing Information.] to AVASTIN (bevacizumab).

1 INDICATIONS AND USAGE

VEGZELMA is a vascular endothelial growth factor inhibitor indicated for the treatment of:

- Metastatic colorectal cancer, in combination with intravenous fluorouracil-based chemotherapy for first- or second-line treatment. (1.1)
- Metastatic colorectal cancer, in combination with fluoropyrimidine-irinotecan- or fluoropyrimidine-oxaliplatin-based chemotherapy for second-line treatment in patients who have progressed on a first-line bevacizumab product-containing regimen. (1.1)

Limitations of Use: VEGZELMA is not indicated for adjuvant treatment of colon cancer. (1.1)

- Unresectable, locally advanced, recurrent or metastatic non-squamous non-small cell lung cancer, in combination with carboplatin and paclitaxel for first-line treatment. (1.2)
- Recurrent glioblastoma in adults. (1.3)
- Metastatic renal cell carcinoma in combination with interferon alfa. (1.4)
- Persistent, recurrent, or metastatic cervical cancer, in combination with paclitaxel and cisplatin, or paclitaxel and topotecan. (1.5)
- Epithelial ovarian, fallopian tube, or primary peritoneal cancer:
  - in combination with carboplatin and paclitaxel, followed by VEGZELMA as a single agent, for stage III or IV disease following initial surgical resection (1.6)
  - in combination with paclitaxel, pegylated liposomal doxorubicin, or topotecan for platinum-resistant recurrent disease who received no more than 2 prior chemotherapy regimens (1.6)
  - in combination with carboplatin and paclitaxel or carboplatin and gemcitabine, followed by VEGZELMA as a single agent, for platinum-sensitive recurrent disease (1.6)

2 DOSAGE AND ADMINISTRATION

Withhold for at least 28 days prior to elective surgery. Do not administer VEGZELMA for 28 days following major surgery and until adequate wound healing. (2.1)

Metastatic colorectal cancer (2.2)

- 5 mg/kg every 2 weeks with bolus-IFL
- 10 mg/kg every 2 weeks with FOLFOX4
- 5 mg/ kg every 2 weeks or 7.5 mg/kg every 3 weeks with fluoropyrimidine-irinotecan- or fluoropyrimidine-oxaliplatin based chemotherapy after progression on a first-line bevacizumab product containing regimen

First-line non−squamous non−small cell lung cancer (2.3)

- 15 mg/kg every 3 weeks with carboplatin and paclitaxel

Recurrent glioblastoma (2.4)

- 10 mg/kg every 2 weeks

Metastatic renal cell carcinoma (2.5)

- 10 mg/kg every 2 weeks with interferon alfa

Persistent, recurrent, or metastatic cervical cancer (2.6)

- 15 mg/kg every 3 weeks with paclitaxel and cisplatin, or paclitaxel and topotecan

Stage III or IV epithelial ovarian, fallopian tube or primary peritoneal cancer following initial surgical resection (2.7)

- 15 mg/kg every 3 weeks with carboplatin and paclitaxel for up to 6 cycles, followed by 15 mg/kg every 3 weeks as a single agent, for a total of up to 22 cycles

Platinum-resistant recurrent epithelial ovarian, fallopian tube or primary peritoneal cancer (2.7)

- 10 mg/kg every 2 weeks with paclitaxel, pegylated liposomal doxorubicin, or topotecan given every week
- 15 mg/kg every 3 weeks with topotecan given every 3 weeks

Platinum-sensitive recurrent epithelial ovarian, fallopian tube, or primary peritoneal cancer (2.7)

- 15 mg/kg every 3 weeks with carboplatin and paclitaxel for 6-8 cycles, followed by 15 mg/kg every 3 weeks as a single agent
- 15 mg/kg every 3 weeks with carboplatin and gemcitabine for 6-10 cycles, followed by 15 mg/kg every 3 weeks as a single agent

Administer as an intravenous infusion after dilution. See full Prescribing Informatio for preparation and administration instructions and dosage modifications for adverse reactions. (2.8 and 2.9)

3 DOSAGE FORMS AND STRENGTHS

Injection: 100 mg/4 mL (25 mg/mL) or 400 mg/16 mL (25 mg/mL) in a single-dose vial (3)

4 CONTRAINDICATIONS

None (4)

5 WARNINGS AND PRECAUTIONS

- Gastrointestinal Perforations and Fistula: Discontinue for gastrointestinal perforations, tracheoesophageal fistula, grade 4 fistula, or fistula formation involving any organ. (5.1)
- Surgery and Wound Healing Complications: In patients who experience wound healing complications during VEGZELMA treatment, withhold VEGZELMA until adequate wound healing. Withhold for at least 28 days prior to elective surgery. Do not administer VEGZELMA for at least 28 days following a major surgery, and until adequate wound healing. The safety of resumption of VEGZELMA after resolution of wound healing complication has not been established. Discontinue for wound healing complications of necrotizing fasciitis. (5.2)
- Hemorrhage: Severe or fatal hemorrhages have occurred. Do not administer for recent hemoptysis. Discontinue for Grade 3–4 hemorrhage. (5.3)
- Arterial Thromboembolic Events (ATE): Discontinue for severe ATE. (5.4)
- Venous Thromboembolic Events (VTE): Discontinue for Grade 4 VTE. (5.5)
- Hypertension: Monitor blood pressure and treat hypertension. Withhold if not medically controlled; resume once controlled. Discontinue for hypertensive crisis or hypertensive encephalopathy. (5.6)
- Posterior Reversible Encephalopathy Syndrome (PRES): Discontinue. (5.7)
- Renal Injury and Proteinuria: Monitor urine protein. Discontinue for nephrotic syndrome. Withhold until less than 2 grams of protein in urine. (5.8)
- Infusion–Related Reactions: Decrease rate for infusion-related reactions. Discontinue for severe infusion-related reactions and administer medical therapy. (5.9)
- Embryo-Fetal Toxicity: May cause fetal harm. Advise females of potential risk to fetus and need for use of effective contraception. (5.10, 8.1, 8.3)
- Ovarian Failure: Advise females of the potential risk. (5.11, 8.3)
- Congestive Heart Failure (CHF): Discontinue VEGZELMA in patients who develop CHF. (5.12)

6 ADVERSE REACTIONS

Most common adverse reactions incidence (incidence >10%) are epistaxis, headache, hypertension, rhinitis, proteinuria, taste alteration, dry skin, hemorrhage, lacrimation disorder, back pain and exfoliative dermatitis. (6.1)

To report SUSPECTED ADVERSE REACTIONS, contact CELLTRION Inc. at 1-833-938-2021 or FDA at 1-800-FDA-1088 or www.fda.gov/medwatch.

8 USE IN SPECIFIC POPULATIONS

Lactation: Advise not to breastfeed. (8.2)

FULL PRESCRIBING INFORMATION

1 INDICATIONS AND USAGE

1.1 Metastatic Colorectal Cancer

VEGZELMA, in combination with intravenous fluorouracil-based chemotherapy, is indicated for the first- or second-line treatment of patients with metastatic colorectal cancer (mCRC).

VEGZELMA, in combination with fluoropyrimidine-irinotecan- or fluoropyrimidine-oxaliplatin-based chemotherapy, is indicated for the second-line treatment of patients with mCRC who have progressed on a first-line bevacizumab product-containing regimen.

Limitations of Use: VEGZELMA is not indicated for adjuvant treatment of colon cancer [see Clinical Studies (14.2)].

1.2 First-Line Non-Squamous Non-Small Cell Lung Cancer

VEGZELMA, in combination with carboplatin and paclitaxel, is indicated for the first-line treatment of patients with unresectable, locally advanced, recurrent or metastatic non–squamous non–small cell lung cancer (NSCLC).

1.3 Recurrent Glioblastoma

VEGZELMA is indicated for the treatment of recurrent glioblastoma (GBM) in adults.

1.4 Metastatic Renal Cell Carcinoma

VEGZELMA, in combination with interferon alfa, is indicated for the treatment of metastatic renal cell carcinoma (mRCC).

1.5 Persistent, Recurrent, or Metastatic Cervical Cancer

VEGZELMA, in combination with paclitaxel and cisplatin or paclitaxel and topotecan, is indicated for the treatment of patients with persistent, recurrent, or metastatic cervical cancer.

1.6 Epithelial Ovarian, Fallopian Tube, or Primary Peritoneal Cancer

VEGZELMA, in combination with carboplatin and paclitaxel, followed by VEGZELMA as a single agent, is indicated for the treatment of patients with stage III or IV epithelial ovarian, fallopian tube, or primary peritoneal cancer following initial surgical resection.

VEGZELMA, in combination with paclitaxel, pegylated liposomal doxorubicin, or topotecan, is indicated for the treatment of patients with platinum-resistant recurrent epithelial ovarian, fallopian tube, or primary peritoneal cancer who received no more than 2 prior chemotherapy regimens.

VEGZELMA, in combination with carboplatin and paclitaxel, or with carboplatin and gemcitabine, followed by VEGZELMA as a single agent, is indicated for the treatment of patients with platinum-sensitive recurrent epithelial ovarian, fallopian tube, or primary peritoneal cancer.

2 DOSAGE AND ADMINISTRATION

2.1 Important Administration Information

Withhold for at least 28 days prior to elective surgery. Do not administer VEGZELMA until at least 28 days following major surgery and until adequate wound healing.

2.2 Metastatic Colorectal Cancer

The recommended dosage when VEGZELMA is administered in combination with intravenous fluorouracil-based chemotherapy is:

- 5 mg/kg intravenously every 2 weeks in combination with bolus-IFL.
- 10 mg/kg intravenously every 2 weeks in combination with FOLFOX4.
- 5 mg/kg intravenously every 2 weeks or 7.5 mg/kg intravenously every 3 weeks in combination with fluoropyrimidine-irinotecan-or fluoropyrimidine-oxaliplatin-based chemotherapy in patients who have progressed on a first-line bevacizumab product-containing regimen.

2.3 First-Line Non-Squamous Non-Small Cell Lung Cancer

The recommended dosage is 15 mg/kg intravenously every 3 weeks in combination with carboplatin and paclitaxel.

2.4 Recurrent Glioblastoma

The recommended dosage is 10 mg/kg intravenously every 2 weeks.

2.5 Metastatic Renal Cell Carcinoma

The recommended dosage is 10 mg/kg intravenously every 2 weeks in combination with interferon alfa.

2.6 Persistent, Recurrent, or Metastatic Cervical Cancer

The recommended dosage is 15 mg/kg intravenously every 3 weeks in combination with paclitaxel and cisplatin or in combination with paclitaxel and topotecan.

2.7 Epithelial Ovarian, Fallopian Tube, or Primary Peritoneal Cancer

Stage III or IV Disease Following Initial Surgical Resection

The recommended dosage is 15 mg/kg intravenously every 3 weeks in combination with carboplatin and paclitaxel for up to 6 cycles, followed by VEGZELMA 15 mg/kg every 3 weeks as a single agent for a total of up to 22 cycles or until disease progression, whichever occurs earlier.

Recurrent Disease

Platinum Resistant

The recommended dosage is 10 mg/kg intravenously every 2 weeks in combination with paclitaxel, pegylated liposomal doxorubicin, or topotecan (every week).

The recommended dosage is 15 mg/kg intravenously every 3 weeks in combination with topotecan (every 3 weeks).

Platinum Sensitive

The recommended dosage is 15 mg/kg intravenously every 3 weeks, in combination with carboplatin and paclitaxel for 6 to 8 cycles, followed by VEGZELMA 15 mg/kg every 3 weeks as a single agent until disease progression.

The recommended dosage is 15 mg/kg intravenously every 3 weeks, in combination with carboplatin and gemcitabine for 6 to 10 cycles, followed by VEGZELMA 15 mg/kg every 3 weeks as a single agent until disease progression.

2.8 Dosage Modifications for Adverse Reactions

Table 1 describes dosage modifications for specific adverse reactions. No dose reductions for VEGZELMA are recommended.

Table 1: Dosage Modifications for Adverse Reactions
Adverse Reaction | Severity | Dosage Modification
Gastrointestinal Perforations and Fistulae [see Warnings and Precautions (5.1)]. | - Gastrointestinal perforation, any grade - Tracheoesophageal fistula, any grade - Fistula, Grade 4 - Fistula formation involving any internal organ | Discontinue VEGZELMA
Wound Healing Complications [see Warnings and Precautions (5.2)]. | - Any | Withhold VEGZELMA until adequate wound healing. The safety of resumption of bevacizumab products after resolution of wound healing complications has not been established.
Wound Healing Complications [see Warnings and Precautions (5.2)]. | - Necrotizing fasciitis | Discontinue VEGZELMA
Hemorrhage [see Warnings and Precautions (5.3)]. | - Grade 3 or 4 | Discontinue VEGZELMA
Hemorrhage [see Warnings and Precautions (5.3)]. | - Recent history of hemoptysis of 1/2 teaspoon (2.5 mL) or more | Withhold VEGZELMA
Thromboembolic Events [see Warnings and Precautions (5.4, 5.5)]. | - Arterial thromboembolism, severe | Discontinue VEGZELMA
Thromboembolic Events [see Warnings and Precautions (5.4, 5.5)]. | - Venous thromboembolism, Grade 4 | Discontinue VEGZELMA
Hypertension [see Warnings and Precautions (5.6)]. | - Hypertensive crisis - Hypertensive encephalopathy | Discontinue VEGZELMA
Hypertension [see Warnings and Precautions (5.6)]. | - Hypertension, severe | Withhold VEGZELMA if not controlled with medical management; resume once controlled
Posterior Reversible Encephalopathy Syndrome (PRES) [see Warnings and Precautions (5.7)]. | - Any | Discontinue VEGZELMA
Renal Injury and Proteinuria [see Warnings and Precautions (5.8)]. | - Nephrotic syndrome | Discontinue VEGZELMA
Renal Injury and Proteinuria [see Warnings and Precautions (5.8)]. | - Proteinuria greater than or equal to 2 grams per 24 hours in absence of nephrotic syndrome | Withhold VEGZELMA until proteinuria less than 2 grams per 24 hours
Infusion-Related Reactions [see Warnings and Precautions (5.9)]. | - Severe | Discontinue VEGZELMA
Infusion-Related Reactions [see Warnings and Precautions (5.9)]. | - Clinically significant | Interrupt infusion; resume at a decreased rate of infusion after symptoms resolve
Infusion-Related Reactions [see Warnings and Precautions (5.9)]. | - Mild, clinically insignificant | Decrease infusion rate
Congestive Heart Failure [see Warnings and Precautions (5.12)]. | - Any | Discontinue VEGZELMA

2.9 Preparation and Administration

Preparation

- Use appropriate aseptic technique.
- Use sterile needle and syringe to prepare VEGZELMA.
- Visually inspect vial for particulate matter and discoloration prior to preparation for administration. Discard vial if solution is cloudy, discolored, or contains particulate matter.
- Withdraw necessary amount of VEGZELMA and dilute in a total volume of 100 mL of 0.9% Sodium Chloride Injection, USP. DO NOT ADMINISTER OR MIX WITH DEXTROSE SOLUTION.
- Discard any unused portion left in a vial, as the product contains no preservatives.
- Diluted VEGZELMA solution may be stored at 2°C to 8°C (36°F to 46°F) for up to 24 hours, or at room temperature up to 30°C (86°F) for up to 4 hours, if not used immediately.
- No incompatibilities between VEGZELMA and polyolefin (polypropylene and polyethylene) bag have been observed.

Administration

- Administer as an intravenous infusion.
- First infusion: Administer infusion over 90 minutes.
- Subsequent infusions: Administer second infusion over 60 minutes if first infusion is tolerated. Administer all subsequent infusions over 30 minutes if second infusion over 60 minutes is tolerated.

3 DOSAGE FORMS AND STRENGTHS

Injection: 100 mg/4 mL (25 mg/mL) or 400 mg/16 mL (25 mg/mL) clear to opalescent, colorless to pale brown solution in a single-dose vial.

4 CONTRAINDICATIONS

None.

5 WARNINGS AND PRECAUTIONS

5.1 Gastrointestinal Perforations and Fistulae

Serious, and sometimes fatal, gastrointestinal perforation occurred at a higher incidence in patients receiving bevacizumab products compared to patients receiving chemotherapy. The incidence ranged from 0.3% to 3% across clinical studies, with the highest incidence in patients with a history of prior pelvic radiation. Perforation can be complicated by intra-abdominal abscess, fistula formation, and the need for diverting ostomies. The majority of perforations occurred within 50 days of the first dose [see Adverse Reactions (6.1)].

Serious fistulae (including, tracheoesophageal, bronchopleural, biliary, vaginal, renal and bladder sites) occurred at a higher incidence in patients receiving bevacizumab products compared to patients receiving chemotherapy. The incidence ranged from <1% to 1.8% across clinical studies, with the highest incidence in patients with cervical cancer. The majority of fistulae occurred within 6 months of the first dose. Patients who develop a gastrointestinal vaginal fistula may also have a bowel obstruction and require surgical intervention, as well as a diverting ostomy.

Avoid VEGZELMA in patients with ovarian cancer who have evidence of recto-sigmoid involvement by pelvic examination or bowel involvement on CT scan or clinical symptoms of bowel obstruction. Discontinue in patients who develop gastrointestinal perforation, tracheoesophageal fistula or any Grade 4 fistula. Discontinue in patients with fistula formation involving any internal organ.

5.2 Surgery and Wound Healing Complications

In a controlled clinical study in which bevacizumab was not administered within 28 days of major surgical procedures, the incidence of wound healing complications, including serious and fatal complications, was 15% in patients with mCRC who underwent surgery while receiving bevacizumab and 4% in patients who did not receive bevacizumab. In a controlled clinical study in patients with relapsed or recurrent GBM, the incidence of wound healing events was 5% in patients who received bevacizumab and 0.7% in patients who did not receive bevacizumab [see Adverse Reactions (6.1)].

In patients who experience wound healing complications during VEGZELMA treatment, withhold VEGZELMA until adequate wound healing. Withhold for at least 28 days prior to elective surgery. Do not administer for at least 28 days following major surgery and until adequate wound healing. The safety of resumption of bevacizumab products after resolution of wound healing complications has not been established [see Dosage and Administration (2.8)].

Necrotizing fasciitis including fatal cases, has been reported in patients receiving bevacizumab, usually secondary to wound healing complications, gastrointestinal perforation or fistula formation. Discontinue VEGZELMA in patients who develop necrotizing fasciitis.

5.3 Hemorrhage

Bevacizumab products can result in two distinct patterns of bleeding: minor hemorrhage, which is most commonly Grade 1 epistaxis, and serious hemorrhage, which in some cases has been fatal. Severe or fatal hemorrhage, including hemoptysis, gastrointestinal bleeding, hematemesis, CNS hemorrhage, epistaxis, and vaginal bleeding occurred up to 5-fold more frequently in patients receiving bevacizumab compared to patients receiving chemotherapy alone. Across clinical studies, the incidence of Grades 3–5 hemorrhagic events ranged from 0.4% to 7% in patients receiving bevacizumab [see Adverse Reactions (6.1)].

Serious or fatal pulmonary hemorrhage occurred in 31% of patients with squamous NSCLC and 4% of patients with non-squamous NSCLC receiving bevacizumab with chemotherapy compared to none of the patients receiving chemotherapy alone.

Do not administer VEGZELMA to patients with recent history of hemoptysis of 1/2 teaspoon or more of red blood. Discontinue in patients who develop a Grades 3–4 hemorrhage.

5.4 Arterial Thromboembolic Events

Serious, sometimes fatal, arterial thromboembolic events (ATE) including cerebral infarction, transient ischemic attacks, myocardial infarction, and angina, occurred at a higher incidence in patients receiving bevacizumab compared to patients receiving chemotherapy. Across clinical studies, the incidence of Grades 3–5 ATE was 5% in patients receiving bevacizumab with chemotherapy compared to ≤2% in patients receiving chemotherapy alone; the highest incidence occurred in patients with GBM. The risk of developing ATE was increased in patients with a history of arterial thromboembolism, diabetes, or >65 years [see Use in Specific Populations (8.5)].

Discontinue in patients who develop a severe ATE. The safety of reinitiating bevacizumab products after an ATE is resolved is not known.

5.5 Venous Thromboembolic Events

An increased risk of venous thromboembolic events (VTE) was observed across clinical studies [see Adverse Reactions (6.1)]. In Study GOG-0240, Grades 3–4 VTE occurred in 11% of patients receiving bevacizumab with chemotherapy compared with 5% of patients receiving chemotherapy alone. In EORTC 26101, the incidence of Grades 3–4 VTE was 5% in patients receiving bevacizumab with chemotherapy compared to 2% in patients receiving chemotherapy alone.

Discontinue VEGZELMA in patients with a Grade 4 VTE, including pulmonary embolism.

5.6 Hypertension

Severe hypertension occurred at a higher incidence in patients receiving bevacizumab products as compared to patients receiving chemotherapy alone. Across clinical studies, the incidence of Grades 3–4 hypertension ranged from 5% to 18%.

Monitor blood pressure every two to three weeks during treatment with VEGZELMA. Treat with appropriate anti-hypertensive therapy and monitor blood pressure regularly. Continue to monitor blood pressure at regular intervals in patients with VEGZELMA-induced or -exacerbated hypertension after discontinuing VEGZELMA. Withhold VEGZELMA in patients with severe hypertension that is not controlled with medical management; resume once controlled with medical management. Discontinue in patients who develop hypertensive crisis or hypertensive encephalopathy.

5.7 Posterior Reversible Encephalopathy Syndrome

Posterior reversible encephalopathy syndrome (PRES) was reported in <0.5% of patients across clinical studies. The onset of symptoms occurred from 16 hours to 1 year after the first dose. PRES is a neurological disorder which can present with headache, seizure, lethargy, confusion, blindness and other visual and neurologic disturbances. Mild to severe hypertension may be present. Magnetic resonance imaging is necessary to confirm the diagnosis of PRES.

Discontinue VEGZELMA in patients who develop PRES. Symptoms usually resolve or improve within days after discontinuing bevacizumab products, although some patients have experienced ongoing neurologic sequelae. The safety of reinitiating bevacizumab products in patients who developed PRES is not known.

5.8 Renal Injury and Proteinuria

The incidence and severity of proteinuria was higher in patients receiving bevacizumab products as compared to patients receiving chemotherapy. Grade 3 (defined as urine dipstick 4+ or >3.5 grams of protein per 24 hours) to Grade 4 (defined as nephrotic syndrome) ranged from 0.7% to 7% in clinical studies.

The overall incidence of proteinuria (all grades) was only adequately assessed in Study BO17705, in which the incidence was 20%. Median onset of proteinuria was 5.6 months (15 days to 37 months) after initiating bevacizumab. Median time to resolution was 6.1 months (95% CI: 2.8, 11.3). Proteinuria did not resolve in 40% of patients after median follow-up of 11.2 months and required discontinuation of bevacizumab in 30% of the patients who developed proteinuria [see Adverse Reactions (6.1)].

In an exploratory, pooled analysis of patients from seven randomized clinical studies, 5% of patients receiving bevacizumab with chemotherapy experienced Grades 2–4 (defined as urine dipstick 2+ or greater or >1 gram of protein per 24 hours or nephrotic syndrome) proteinuria. Grades 2–4 proteinuria resolved in 74% of patients. Bevacizumab was reinitiated in 42% of patients. Of the 113 patients who reinitiated bevacizumab, 48% experienced a second episode of Grades 2–4 proteinuria.

Nephrotic syndrome occurred in <1% of patients receiving bevacizumab across clinical studies, in some instances with fatal outcome. In a published case series, kidney biopsy of 6 patients with proteinuria showed findings consistent with thrombotic microangiopathy. Results of a retrospective analysis of 5805 patients who received bevacizumab with chemotherapy and 3713 patients who received chemotherapy alone, showed higher rates of elevated serum creatinine levels (between 1.5 to 1.9 times baseline levels) in patients who received bevacizumab. Serum creatinine levels did not return to baseline in approximately one-third of patients who received bevacizumab.

Monitor proteinuria by dipstick urine analysis for the development or worsening of proteinuria with serial urinalyses during VEGZELMA therapy. Patients with a 2+ or greater urine dipstick reading should undergo further assessment with a 24-hour urine collection. Withhold for proteinuria greater than or equal to 2 grams per 24 hours and resume when less than 2 grams per 24 hours. Discontinue in patients who develop nephrotic syndrome.

Data from a postmarketing safety study showed poor correlation between UPCR (Urine Protein/Creatinine Ratio) and 24-hour urine protein [Pearson Correlation 0.39 (95% CI: 0.17, 0.57)].

5.9 Infusion-Related Reactions

Infusion-related reactions reported across clinical studies and postmarketing experience include hypertension, hypertensive crises associated with neurologic signs and symptoms, wheezing, oxygen desaturation, Grade 3 hypersensitivity, anaphylatoid/anaphylactic reacionts, chest pain, headaches, rigors, and diaphoresis. In clinical studies, infusion-related reactions with the first dose occurred in <3% of patients and severe reactions occurred in 0.4% of patients.

Decrease the rate of infusion for mild, clinically insignificant infusion-related reactions. Interrupt the infusion in patients with clinically significant infusion-related reactions and consider resuming at a slower rate following resolution. Discontinue in patients who develop a severe infusion-related reaction and administer appropriate medical therapy (e.g., epinephrine, corticosteroids, intravenous antihistamines, bronchodilators and/or oxygen).

5.10 Embryo-Fetal Toxicity

Based on its mechanism of action and findings from animal studies, bevacizumab products may cause fetal harm when administered to pregnant women. Congenital malformations were observed with the administration of bevacizumab to pregnant rabbits during organogenesis every 3 days at a dose as low as a clinical dose of 10 mg/kg.

Furthermore, animal models link angiogenesis and VEGF and VEGFR2 to critical aspects of female reproduction, embryo-fetal development, and postnatal development. Advise pregnant women of the potential risk to a fetus. Advise females of reproductive potential to use effective contraception during treatment with VEGZELMA and for 6 months after the last dose [see Use in Specific Populations (8.1, 8.3)].

5.11 Ovarian Failure

The incidence of ovarian failure was 34% vs. 2% in premenopausal women receiving bevacizumab with chemotherapy as compared to those receiving chemotherapy alone for adjuvant treatment of a solid tumor. After discontinuing bevacizumab, recovery of ovarian function at all time points during the post-treatment period was demonstrated in 22% of women receiving bevacizumab. Recovery of ovarian function is defined as resumption of menses, a positive serum β-HCG pregnancy test, or an FSH level <30 mIU/mL during the post-treatment period. Long-term effects of bevacizumab products on fertility are unknown. Inform females of reproductive potential of the risk of ovarian failure prior to initiating VEGZELMA [see Adverse Reactions (6.1), Use in Specific Populations (8.3)].

5.12 Congestive Heart Failure (CHF)

VEGZELMA is not indicated for use with anthracycline-based chemotherapy. The incidence of Grade ≥3 left ventricular dysfunction was 1% in patients receiving bevacizumab compared to 0.6% of patients receiving chemotherapy alone. Among patients who received prior anthracycline treatment, the rate of CHF was 4% for patients receiving bevacizumab with chemotherapy as compared to 0.6% for patients receiving chemotherapy alone.

In previously untreated patients with a hematological malignancy, the incidence of CHF and decline in left ventricular ejection fraction (LVEF) were increased in patients receiving bevacizumab with anthracycline-based chemotherapy compared to patients receiving placebo with the same chemotherapy regimen. The proportion of patients with a decline in LVEF from baseline of ≥20% or a decline from baseline of 10% to <50%, was 10% in patients receiving bevacizumab with chemotherapy compared to 5% in patients receiving chemotherapy alone. Time to onset of left-ventricular dysfunction or CHF was 1 to 6 months after the first dose in at least 85% of the patients and was resolved in 62% of the patients who developed CHF in the bevacizumab arm compared to 82% in the placebo arm. Discontinue VEGZELMA in patients who develop CHF.

6 ADVERSE REACTIONS

The following clinically significant adverse reactions are described elsewhere in the labeling:

- Gastrointestinal Perforations and Fistulae [see Warnings and Precautions (5.1)].
- Surgery and Wound Healing Complications [see Warnings and Precautions (5.2)].
- Hemorrhage [see Warnings and Precautions (5.3)].
- Arterial Thromboembolic Events [see Warnings and Precautions (5.4)].
- Venous Thromboembolic Events [see Warnings and Precautions (5.5)].
- Hypertension [see Warnings and Precautions (5.6)].
- Posterior Reversible Encephalopathy Syndrome [see Warnings and Precautions (5.7)].
- Renal Injury and Proteinuria [see Warnings and Precautions (5.8)].
- Infusion-Related Reactions [see Warnings and Precautions (5.9)].
- Ovarian Failure [see Warnings and Precautions (5.11)].
- Congestive Heart Failure [see Warnings and Precautions (5.12)].

6.1 Clinical Trials Experience

Because clinical studies are conducted under widely varying conditions, adverse reaction rates observed in the clinical studies of a drug cannot be directly compared to rates in the clinical studies of another drug and may not reflect the rates observed in practice.

The safety data in Warnings and Precautions and described below reflect exposure to bevacizumab in 4463 patients including those with mCRC (AVF2107g, E3200), non-squamous NSCLC (E4599), GBM (EORTC 26101), mRCC (BO17705), cervical cancer (GOG-0240), epithelial ovarian, fallopian tube, or primary peritoneal cancer (MO22224, AVF4095, GOG-0213, and GOG-0218) or another cancer at the recommended dose and schedule for a median of 6 to 23 doses. The most common adverse reactions observed in patients receiving bevacizumab as a single agent or in combination with other anti-cancer therapies at a rate >10% were epistaxis, headache, hypertension, rhinitis, proteinuria, taste alteration, dry skin, hemorrhage, lacrimation disorder, back pain, and exfoliative dermatitis.

Across clinical studies, bevacizumab was discontinued in 8% to 22% of patients because of adverse reactions [see Clinical Studies (14)].

Metastatic Colorectal Cancer

In Combination with bolus-IFL

The safety of bevacizumab was evaluated in 392 patients who received at least one dose of bevacizumab in a double-blind, active-controlled study (AVF2107g), which compared bevacizumab (5 mg/kg every 2 weeks) with bolus-IFL to placebo with bolus-IFL in patients with mCRC [see Clinical Studies (14.1)]. Patients were randomized (1:1:1) to placebo with bolus-IFL, bevacizumab with bolus-IFL, or bevacizumab with fluorouracil and leucovorin. The demographics of the safety population were similar to the demographics of the efficacy population. All Grades 3-4 adverse reactions and selected Grades 1-2 adverse reactions (i.e., hypertension, proteinuria, thromboembolic events) were collected in the entire study population. Adverse reactions are presented in Table 2.

Table 2: Grades 3–4 Adverse Reactions Occurring at Higher Incidence (≥2%) in Patients Receiving Bevacizumab vs. Placebo in Study AVF2107g
Adverse Reaction [NCI-CTC version 3] | Bevacizumab with IFL (N=392) | Placebo with IFL (N=396)
Hematology
Leukopenia | 37% | 31%
Neutropenia | 21% | 14%
Gastrointestinal
Diarrhea | 34% | 25%
Abdominal pain | 8% | 5%
Constipation | 4% | 2%
Vascular
Hypertension | 12% | 2%
Deep vein thrombosis | 9% | 5%
Intra-abdominal thrombosis | 3% | 1%
Syncope | 3% | 1%
General
Asthenia | 10% | 7%
Pain | 8% | 5%

In Combination with FOLFOX4

The safety of bevacizumab was evaluated in 521 patients in an open-label, active-controlled study (E3200) in patients who were previously treated with irinotecan and fluorouracil for initial therapy for mCRC. Patients were randomized (1:1:1) to FOLFOX4, bevacizumab (10 mg/kg every 2 weeks prior to FOLFOX4 on Day 1) with FOLFOX4, or bevacizumab alone (10 mg/kg every 2 weeks). Bevacizumab was continued until disease progression or unacceptable toxicity.

The demographics of the safety population were similar to the demographics of the efficacy population.

Selected Grades 3–5 non-hematologic and Grades 4–5 hematologic occurring at a higher incidence (≥2%) in patients receiving bevacizumab with FOLFOX4 compared to FOLFOX4 alone were fatigue (19% vs. 13%), diarrhea (18% vs. 13%), sensory neuropathy (17% vs. 9%), nausea (12% vs. 5%), vomiting (11% vs. 4%), dehydration (10% vs. 5%), hypertension (9% vs. 2%), abdominal pain (8% vs. 5%), hemorrhage (5% vs. 1%), other neurological (5% vs. 3%), ileus (4% vs. 1%) and headache (3% vs. 0%). These data are likely to under-estimate the true adverse reaction rates due to the reporting mechanisms.

First-Line Non Squamous Non-Small Cell Lung Cancer

The safety of bevacizumab was evaluated as first-line treatment in 422 patients with unresectable NSCLC who received at least one dose of bevacizumab in an active-controlled, open-label, multicenter trial (E4599) [see Clinical Studies (14.3)]. Chemotherapy naïve patients with locally advanced, metastatic or recurrent non–squamous NSCLC were randomized (1:1) to receive six 21-day cycles of paclitaxel and carboplatin with or without bevacizumab (15 mg/kg every 3 weeks). After completion or upon discontinuation of chemotherapy, patients randomized to receive bevacizumab continued to receive bevacizumab alone until disease progression or until unacceptable toxicity. The trial excluded patients with predominant squamous histology (mixed cell type tumors only), CNS metastasis, gross hemoptysis (1/2 teaspoon or more of red blood), unstable angina, or receiving therapeutic anticoagulation. The demographics of the safety population were similar to the demographics of the efficacy population.

Only Grades 3–5 non-hematologic and Grades 4–5 hematologic adverse reactions were collected. Grades 3–5 non-hematologic and Grades 4–5 hematologic adverse reactions occurring at a higher incidence (≥2%) in patients receiving bevacizumab with paclitaxel and carboplatin compared with patients receiving chemotherapy alone were neutropenia (27% vs. 17%), fatigue (16% vs. 13%), hypertension (8% vs. 0.7%), infection without neutropenia (7% vs. 3%), venous thromboembolism (5% vs. 3%), febrile neutropenia (5% vs. 2%), pneumonitis/pulmonary infiltrates (5% vs. 3%), infection with Grade 3 or 4 neutropenia (4% vs. 2%), hyponatremia (4% vs. 1%), headache (3% vs. 1%) and proteinuria (3% vs. 0%).

Recurrent Glioblastoma

The safety of bevacizumab was evaluated in a multicenter, randomized, open-label study (EORTC 26101) in patients with recurrent GBM following radiotherapy and temozolomide of whom 278 patients received at least one dose of bevacizumab and are considered safety evaluable [see Clinical Studies (14.4)]. Patients were randomized (2:1) to receive bevacizumab (10 mg/kg every 2 weeks) with lomustine or lomustine alone until disease progression or unacceptable toxicity. The demographics of the safety population were similar to the demographics of the efficacy population. In the bevacizumab with lomustine arm, 22% of patients discontinued treatment due to adverse reactions compared with 10% of patients in the lomustine arm. In patients receiving bevacizumab with lomustine, the adverse reaction profile was similar to that observed in other approved indications.

Metastatic Renal Cell Carcinoma

The safety of bevacizumab was evaluated in 337 patients who received at least one dose of bevacizumab in a multicenter, double-blind study (BO17705) in patients with mRCC. Patients who had undergone a nephrectomy were randomized (1:1) to receive either bevacizumab (10 mg/kg every 2 weeks) or placebo with interferon alfa [see Clinical Studies (14.5)]. Patients were treated until disease progression or unacceptable toxicity. The demographics of the safety population were similar to the demographics of the efficacy population.

Grades 3–5 adverse reactions occurring at a higher incidence (>2%) were fatigue (13% vs. 8%), asthenia (10% vs. 7%), proteinuria (7% vs. 0%), hypertension (6% vs. 1%; including hypertension and hypertensive crisis), and hemorrhage (3% vs. 0.3%; including epistaxis, small intestinal hemorrhage, aneurysm ruptured, gastric ulcer hemorrhage, gingival bleeding, hemoptysis, hemorrhage intracranial, large intestinal hemorrhage, respiratory tract hemorrhage, and traumatic hematoma). Adverse reactions are presented in Table 3.

Table 3: Grades 1–5 Adverse Reactions Occurring at Higher Incidence (≥5%) of Patients Receiving Bevacizumab vs. Placebo with Interferon Alfa in Study BO17705
Adverse Reaction* | Bevacizumab with Interferon Alfa (N=337) | Placebo with Interferon Alfa (N=304)
Metabolism and nutrition
Decreased appetite | 36% | 31%
Weight loss | 20% | 15%
General
Fatigue | 33% | 27%
Vascular
Hypertension | 28% | 9%
Respiratory, thoracic and mediastinal
Epistaxis | 27% | 4%
Dysphonia | 5% | 0%
Nervous system
Headache | 24% | 16%
Gastrointestinal
Diarrhea | 21% | 16%
Renal and urinary
Proteinuria | 20% | 3%
Musculoskeletal and connective tissue
Myalgia | 19% | 14%
Back pain | 12% | 6%

The following adverse reactions were reported at a 5-fold greater incidence in patients receiving bevacizumab with interferon-alfa compared to patients receiving placebo with interferon-alfa and not represented in Table 3: gingival bleeding (13 patients vs. 1 patient); rhinitis (9 vs. 0); blurred vision (8 vs. 0); gingivitis (8 vs. 1); gastroesophageal reflux disease (8 vs. 1); tinnitus (7 vs. 1); tooth abscess (7 vs. 0); mouth ulceration (6 vs. 0); acne (5 vs. 0); deafness (5 vs. 0); gastritis (5 vs. 0); gingival pain (5 vs. 0) and pulmonary embolism (5 vs. 1).

Persistent, Recurrent, or Metastatic Cervical Cancer

The safety of bevacizumab was evaluated in 218 patients who received at least one dose of bevacizumab in a multicenter study (GOG-0240) in patients with persistent, recurrent, or metastatic cervical cancer [see Clinical Studies (14.6)]. Patients were randomized (1:1:1:1) to receive paclitaxel and cisplatin with or without bevacizumab (15 mg/kg every 3 weeks), or paclitaxel and topotecan with or without bevacizumab (15 mg/kg every 3 weeks). The demographics of the safety population were similar to the demographics of the efficacy population.

Grades 3–4 adverse reactions occurring at a higher incidence (≥2%) in 218 patients receiving bevacizumab with chemotherapy compared to 222 patients receiving chemotherapy alone were abdominal pain (12% vs. 10%), hypertension (11% vs. 0.5%), thrombosis (8% vs. 3%), diarrhea (6% vs. 3%), anal fistula (4% vs. 0%), proctalgia (3% vs. 0%), urinary tract infection (8% vs. 6%), cellulitis (3% vs. 0.5%), fatigue (14% vs. 10%), hypokalemia (7% vs. 4%), hyponatremia (4% vs. 1%), dehydration (4% vs. 0.5%), neutropenia (8% vs. 4%), lymphopenia (6% vs. 3%), back pain (6% vs. 3%), and pelvic pain (6% vs. 1%). Adverse reactions are presented in Table 4.

Table 4: Grades 1–4 Adverse Reactions Occurring at Higher Incidence (≥ 5%) in Patients Receiving Bevacizumab with Chemotherapy vs. Chemotherapy Alone in Study GOG-0240
Adverse Reaction* | Bevacizumab with Chemotherapy (N=218) | Chemotherapy (N=222)
General
Fatigue | 80% | 75%
Peripheral edema | 15% | 22%
Metabolism and nutrition
Decreased appetite | 34% | 26%
Hyperglycemia | 26% | 19%
Hypomagnesemia | 24% | 15%
Weight loss | 21% | 7%
Hyponatremia | 19% | 10%
Hypoalbuminemia | 16% | 11%
Vascular
Hypertension | 29% | 6%
Thrombosis | 10% | 3%
Infections
Urinary tract infection | 22% | 14%
Infection | 10% | 5%
Nervous system
Headache | 22% | 13%
Dysarthria | 8% | 1%
Psychiatric
Anxiety | 17% | 10%
Respiratory, thoracic and mediastinal
Epistaxis | 17% | 1%
Renal and urinary
Increased blood creatinine | 16% | 10%
Proteinuria | 10% | 3%
Gastrointestinal
Stomatitis | 15% | 10%
Proctalgia | 6% | 1%
Anal fistula | 6% | 0%
Reproductive system and breast
Pelvic pain | 14% | 8%
Hematology
Neutropenia | 12% | 6%
Lymphopenia | 12% | 5%

Epithelial Ovarian, Fallopian Tube, or Primary Peritoneal Cancer

Stage III or IV Following Initial Surgical Resection

The safety of bevacizumab was evaluated in GOG-0218, a multicenter, randomized, double-blind, placebo controlled, three arm study, which evaluated the addition of bevacizumab to carboplatin and paclitaxel for the treatment of patients with stage III or IV epithelial ovarian, fallopian tube or primary peritoneal cancer following initial surgical resection [see Clinical Studies (14.7)]. Patients were randomized (1:1:1) to carboplatin and paclitaxel without bevacizumab (CPP), carboplatin and paclitaxel with bevacizumab for up to six cycles (CPB15), or carboplatin and paclitaxel with bevacizumab for six cycles followed by bevacizumab as a single agent for up to 16 additional doses (CPB15+). Bevacizumab was given at 15 mg/kg every three weeks. On this trial, 1215 patients received at least one dose of bevacizumab. The demographics of the safety population were similar to the demographics of the efficacy population.

Grades 3-4 adverse reactions occurring at a higher incidence (2%) in either of the bevacizumab arms versus the control arm were fatigue (CPB15+ -9%, CPB15 -6%, CPP -6%), hypertension (CPB15+ -10%, CPB15 -6%,CPP -2%), thrombocytopenia (CPB15+ -21%, CPB15 -20%, CPP -15%) and leukopenia (CPB15+ -51%,CPB15 -53%, CPP -50%). Adverse reactions are presented in Table 5.

Table 5: Grades 1–5 Adverse Reactions Occurring at Higher Incidence (≥ 5%) in Patients Receiving Bevacizumab with Chemotherapy vs. Chemotherapy Alone in Study GOG-0218
Adverse Reaction [NCI-CTC version 3] | Bevacizumab with carboplatin and paclitaxel followed by bevacizumab alone [CPB15+] (N=608) | Bevacizumab with carboplatin and paclitaxel [CPB15] (N=607) | Carboplatin and paclitaxel [CPP] (N=602)
General
Fatigue | 80% | 72% | 73%
Gastrointestinal
Nausea | 58% | 53% | 51%
Diarrhea | 38% | 40% | 34%
Stomatitis | 25% | 19% | 14%
Musculoskeletal and connective tissue
Arthralgia | 41% | 33% | 35%
Pain in extremity | 25% | 19% | 17%
Muscular weakness | 15% | 13% | 9%
Nervous system
Headache | 34% | 26% | 21%
Dysarthria | 12% | 10% | 2%
Vascular
Hypertension | 32% | 24% | 14%
Respiratory, thoracic and mediastinal
Epistaxis | 31% | 30% | 9%
Dyspnea | 26% | 28% | 20%
Nasal mucosal disorder | 10% | 7% | 4%

Platinum-Resistant Recurrent Epithelial Ovarian, Fallopian Tube, or Primary Peritoneal Cancer

The safety of bevacizumab was evaluated in 179 patients who received at least one dose of bevacizumab in a multicenter, open-label study (MO22224) in which patients were randomized (1:1) to bevacizumab with chemotherapy or chemotherapy alone in patients with platinum resistant recurrent epithelial ovarian, fallopian tube, or primary peritoneal cancer that recurred within <6 months from the most recent platinum based therapy [see Clinical Studies (14.8)]. Patients were randomized to receive bevacizumab 10 mg/kg every 2 weeks or 15 mg/kg every 3 weeks. Patients had received no more than 2 prior chemotherapy regimens. The trial excluded patients with evidence of recto-sigmoid involvement by pelvic examination or bowel involvement on CT scan or clinical symptoms of bowel obstruction. Patients were treated until disease progression or unacceptable toxicity. Forty percent of patients on the chemotherapy alone arm received bevacizumab alone upon progression. The demographics of the safety population were similar to the demographics of the efficacy population.

Grades 3-4 adverse reactions occurring at a higher incidence (≥ 2%) in 179 patients receiving bevacizumab with chemotherapy compared to 181 patients receiving chemotherapy alone were hypertension (6.7% vs. 1.1%) and palmar-plantar erythrodysaesthesia syndrome (4.5% vs. 1.7%). Adverse reactions are presented in Table 6.

Table 6: Grades 2–4 Adverse Reactions Occurring at Higher Incidence (≥ 5%) in Patients Receiving Bevacizumab with Chemotherapy vs. Chemotherapy Alone in Study MO22224
Adverse Reaction [NCI-CTC version 3] | Bevacizumab with Chemotherapy (N=179) | Chemotherapy (N=181)
Hematology
Neutropenia | 31% | 25%
Vascular
Hypertension | 19% | 6%
Nervous system
Peripheral sensory neuropathy | 18% | 7%
General
Mucosal inflammation | 13% | 6%
Renal and urinary
Proteinuria | 12% | 0.6%
Skin and subcutaneous tissue
Palmar-plantar erythrodysaesthesia | 11% | 5%
Infections
Infection | 11% | 4%
Respiratory, thoracic and mediastinal
Epistaxis | 5% | 0%

Platinum-Sensitive Recurrent Epithelial Ovarian, Fallopian Tube, or Primary Peritoneal Cancer

Study AVF4095g

The safety of bevacizumab was evaluated in 247 patients who received at least one dose of bevacizumab in a double-blind study (AVF4095g) in patients with platinum sensitive recurrent epithelial ovarian, fallopian tube or primary peritoneal cancer [see Clinical Studies (14.9]. Patients were randomized (1:1) to receive bevacizumab (15 mg/kg) or placebo every 3 weeks with carboplatin and gemcitabine for 6 to 10 cycles followed by bevacizumab or placebo alone until disease progression or unacceptable toxicity. The demographics of the safety population were similar to the demographics of the efficacy population.

Grades 3-4 adverse reactions occurring at a higher incidence (≥ 2%) in patients receiving bevacizumab with chemotherapy compared to placebo with chemotherapy were: thrombocytopenia (40% vs. 34%), nausea (4% vs. 1.3%), fatigue (6% vs. 4%), headache (4% vs. 0.9%), proteinuria (10% vs. 0.4%), dyspnea (4% vs. 1.7%), epistaxis (5% vs. 0.4%), and hypertension (17% vs. 0.9%). Adverse reactions are presented in Table 7.

Table 7: Grades 1–5 Adverse Reactions Occurring at Higher Incidence (≥ 5%) in Patients Receiving Bevacizumab with Chemotherapy vs. Placebo with Chemotherapy in Study AVF4095g
Adverse Reaction [NCI-CTC version 3] | Bevacizumab with Carboplatin and Gemcitabine (N=247) | Placebo with Carboplatin and Gemcitabine (N=233)
General
Fatigue | 82% | 75%
Mucosal inflammation | 15% | 10%
Gastrointestinal
Nausea | 72% | 66%
Diarrhea | 38% | 29%
Stomatitis | 15% | 7%
Hemorrhoids | 8% | 3%
Gingival bleeding | 7% | 0%
Hematology
Thrombocytopenia | 58% | 51%
Respiratory, thoracic and mediastinal
Epistaxis | 55% | 14%
Dyspnea | 30% | 24%
Cough | 26% | 18%
Oropharyngeal pain | 16% | 10%
Dysphonia | 13% | 3%
Rhinorrhea | 10% | 4%
Sinus congestion | 8% | 2%
Nervous system
Headache | 49% | 30%
Dizziness | 23% | 17%
Vascular
Hypertension | 42% | 9%
Musculoskeletal and connective tissue
Arthralgia | 28% | 19%
Back pain | 21% | 13%
Psychiatric
Insomnia | 21% | 15%
Renal and urinary
Proteinuria | 20% | 3%
Injury and procedural
Contusion | 17% | 9%
Infections
Sinusitis | 15% | 9%

Study GOG-0213

The safety of bevacizumab was evaluated in an open-label, controlled study (GOG-0213) in 325 patients with platinum-sensitive recurrent epithelial ovarian, fallopian tube, or primary peritoneal cancer, who have not received more than one previous regimen of chemotherapy [see Clinical Studies (14.9)]. Patients were randomized (1:1) to receive carboplatin and paclitaxel for 6 to 8 cycles or bevacizumab (15 mg/kg every 3 weeks) with carboplatin and paclitaxel for 6 to 8 cycles followed by bevacizumab as a single agent until disease progression or unacceptable toxicity. The demographics of the safety population were similar to the demographics of the efficacy population.

Grades 3-4 adverse reactions occurring at a higher incidence (≥ 2%) in patients receiving bevacizumab with chemotherapy compared to chemotherapy alone were: hypertension (11% vs. 0.6%), fatigue (8% vs. 3%), febrile neutropenia (6% vs. 3%), proteinuria (8% vs. 0%), abdominal pain (6% vs. 0.9%), hyponatremia (4% vs. 0.9%), headache (3% vs. 0.9%), and pain in extremity (3% vs. 0%). Adverse reactions are presented in Table 8.

Table 8: Grades 1–5 Adverse Reactions Occurring at Higher Incidence (≥ 5%) in Patients Receiving Bevacizumab with Chemotherapy vs. Chemotherapy Alone in Study GOG-0213
Adverse Reaction [NCI-CTC version 3] | Bevacizumab with Carboplatin and Paclitaxel (N=325) | Carboplatin and Paclitaxel (N=332)
Musculoskeletal and connective tissue
Arthralgia | 45% | 30%
Myalgia | 29% | 18%
Pain in extremity | 25% | 14%
Back pain | 17% | 10%
Muscular weakness | 13% | 8%
Neck pain | 9% | 0%
Vascular
Hypertension | 42% | 3%
Gastrointestinal
Diarrhea | 39% | 32%
Abdominal pain | 33% | 28%
Vomiting | 33% | 25%
Stomatitis | 33% | 16%
Nervous system
Headache | 38% | 20%
Dysarthria | 14% | 2%
Dizziness | 13% | 8%
Metabolism and nutrition
Decreased appetite | 35% | 25%
Hyperglycemia | 31% | 24%
Hypomagnesemia | 27% | 17%
Hyponatremia | 17% | 6%
Weight loss | 15% | 4%
Hypocalcemia | 12% | 5%
Hypoalbuminemia | 11% | 6%
Hyperkalemia | 9% | 3%
Respiratory, thoracic and mediastinal
Epistaxis | 33% | 2%
Dyspnea | 30% | 25%
Cough | 30% | 17%
Rhinitis allergic | 17% | 4%
Nasal mucosal disorder | 14% | 3%
Skin and subcutaneous tissue
Exfoliative rash | 23% | 16%
Nail disorder | 10% | 2%
Dry skin | 7% | 2%
Renal and urinary
Proteinuria | 17% | 1%
Increased blood creatinine | 13% | 5%
Hepatic
Increased aspartate aminotransferase | 15% | 9%
General
Chest pain | 8% | 2%
Infections
Sinusitis | 7% | 2%

6.2 Immunogenicity

As with all therapeutic proteins, there is a potential for immunogenicity. The detection of antibody formation is highly dependent on the sensitivity and the specificity of the assay. Additionally, the observed incidence of antibody (including neutralizing antibody) positivity in an assay may be influenced by several factors, including assay methodology, sample handling, timing of sample collection, concomitant medications, and underlying disease. For these reasons, comparison of the incidence of antibodies in the studies described below with the incidence of antibodies in other studies or to other bevacizumab products may be misleading.

In clinical studies for adjuvant treatment of a solid tumor, 0.6% (14/2233) of patients tested positive for treatment-emergent anti-bevacizumab antibodies as detected by an electrochemiluminescent (ECL) based assay. Among these 14 patients, three tested positive for neutralizing antibodies against bevacizumab using an enzyme-linked immunosorbent assay (ELISA). The clinical significance of these anti-bevacizumab antibodies is not known.

6.3 Postmarketing Experience

The following adverse reactions have been identified during postapproval use of bevacizumab. Because these reactions are reported voluntarily from a population of uncertain size, it is not always possible to reliably estimate their frequency or establish a causal relationship to drug exposure.

General: Polyserositis

Cardiovascular: Pulmonary hypertension, Mesenteric venous occlusion

Gastrointestinal: Gastrointestinal ulcer, Intestinal necrosis, Anastomotic ulceration

Hemic and lymphatic: Pancytopenia

Hepatobiliary disorders: Gallbladder perforation

Musculoskeletal and Connective Tissue Disorders: Osteonecrosis of the jaw

Renal: Renal thrombotic microangiopathy (manifested as severe proteinuria)

Respiratory: Nasal septum perforation

Vascular: Arterial (including aortic) aneurysms, dissections, and rupture

7 DRUG INTERACTIONS

Effects of VEGZELMA on Other Drugs

No clinically meaningful effect on the pharmacokinetics of irinotecan or its active metabolite SN38, interferon alfa, carboplatin or paclitaxel was observed when bevacizumab was administered in combination with these drugs; however, 3 of the 8 patients receiving bevacizumab with paclitaxel and carboplatin had lower paclitaxel exposure after four cycles of treatment (at Day 63) than those at Day 0, while patients receiving paclitaxel and carboplatin alone had a greater paclitaxel exposure at Day 63 than at Day 0.

8 USE IN SPECIFIC POPULATIONS

8.1 Pregnancy

Risk Summary

Based on findings from animal studies and their mechanism of action [see Clinical Pharmacology (12.1)], bevacizumab products may cause fetal harm in pregnant women. Limited postmarketing reports describe cases of fetal malformations with use of bevacizumab products in pregnancy; however, these reports are insufficient to determine drug-associated risks. In animal reproduction studies, intravenous administration of bevacizumab to pregnant rabbits every 3 days during organogenesis at doses approximately 1 to 10 times the clinical dose of 10 mg/kg produced fetal resorptions, decreased maternal and fetal weight gain and multiple congenital malformations including corneal opacities and abnormal ossification of the skull and skeleton including limb and phalangeal defects (see Data). Furthermore, animal models link angiogenesis and VEGF and VEGFR2 to critical aspects of female reproduction, embryofetal development, and postnatal development. Advise pregnant women of the potential risk to a fetus.

In the U.S. general population, the estimated background risk of major birth defects and miscarriage in clinically recognized pregnancies is 2% to 4% and 15% to 20%, respectively.

Data

Animal Data

Pregnant rabbits dosed with 10 mg/kg to 100 mg/kg bevacizumab (approximately 1 to 10 times the clinical dose of 10 mg/kg) every three days during the period of organogenesis (gestation day 6–18) exhibited decreases in maternal and fetal body weights and increased number of fetal resorptions. There were dose-related increases in the number of litters containing fetuses with any type of malformation (42% for the 0 mg/kg dose, 76% for the 30 mg/kg dose, and 95% for the 100 mg/kg dose) or fetal alterations (9% for the 0 mg/kg dose, 15% for the 30 mg/kg dose, and 61% for the 100 mg/kg dose). Skeletal deformities were observed at all dose levels, with some abnormalities including meningocele observed only at the 100 mg/kg dose level. Teratogenic effects included: reduced or irregular ossification in the skull, jaw, spine, ribs, tibia and bones of the paws; fontanel, rib and hindlimb deformities; corneal opacity; and absent hindlimb phalanges.

8.2 Lactation

Risk Summary

No data are available regarding the presence of bevacizumab products in human milk, the effects on the breast fed infant, or the effects on milk production. Human IgG is present in human milk, but published data suggest that breast milk antibodies do not enter the neonatal and infant circulation in substantial amounts. Because of the potential for serious adverse reactions in breastfed infants, advise women not to breastfeed during treatment with VEGZELMA and for 6 months after the last dose.

8.3 Females and Males of Reproductive Potential

Contraception

Females

Bevacizumab products may cause fetal harm when administered to a pregnant woman [see Use in Specific Populations (8.1)]. Advise females of reproductive potential to use effective contraception during treatment with VEGZELMA and for 6 months after the last dose.

Infertility

Females

Bevacizumab products increase the risk of ovarian failure and may impair fertility. Inform females of reproductive potential of the risk of ovarian failure prior to the first-dose of VEGZELMA. Long-term effects of bevacizumab products on fertility are not known.

In a clinical study of 179 premenopausal women randomized to receive chemotherapy with or without bevacizumab, the incidence of ovarian failure was higher in patients who received bevacizumab with chemotherapy (34%) compared to patients who received chemotherapy alone (2%). After discontinuing bevacizumab with chemotherapy, recovery of ovarian function occurred in 22% of these patients [see Warnings and Precautions (5.11), Adverse Reactions (6.1)].

8.4 Pediatric Use

The safety and effectiveness of bevacizumab products in pediatric patients have not been established. In published literature reports, cases of non-mandibular osteonecrosis have been observed in patients under the age of 18 years who received bevacizumab. Bevacizumab products are not approved for use in patients under the age of 18 years.

Antitumor activity was not observed among eight pediatric patients with relapsed GBM who received bevacizumab and irinotecan. Addition of bevacizumab to standard of care did not result in improved event-free survival in pediatric patients enrolled in two randomized clinical studies, one in high grade glioma (n=121) and one in metastatic rhabdomyosarcoma or non-rhabdomyosarcoma soft tissue sarcoma (n=154).

Based on the population pharmacokinetics analysis of data from 152 pediatric and young adult patients with cancer (7 months to 21 years of age), bevacizumab clearance normalized by body weight in pediatrics was comparable to that in adults.

Juvenile Animal Toxicity Data

Juvenile cynomolgus monkeys with open growth plates exhibited physeal dysplasia following 4 to 26 weeks exposure at 0.4 to 20 times the recommended human dose (based on mg/kg and exposure). The incidence and severity of physeal dysplasia were dose-related and were partially reversible upon cessation of treatment.

8.5 Geriatric Use

In an exploratory, pooled analysis of 1745 patients from five randomized, controlled studies, 35% of patients were ≥65 years old. The overall incidence of ATE was increased in all patients receiving bevacizumab with chemotherapy as compared to those receiving chemotherapy alone, regardless of age; however, the increase in the incidence of ATE was greater in patients ≥65 years (8% vs. 3%) as compared to patients <65 years (2% vs. 1%) [see Warnings and Precautions (5.4)].

11 DESCRIPTION

Bevacizumab-adcd is a vascular endothelial growth factor inhibitor. Bevacizumab-adcd is a recombinant humanized monoclonal IgG1 antibody that contains human framework regions and murine complementarity-determining regions. Bevacizumab-adcd has an approximate molecular weight of 149 kDa. Bevacizumab-adcd is produced in a mammalian cell (Chinese Hamster Ovary) expression system.

VEGZELMA (bevacizumab-adcd) injection is a sterile, preservative-free, clear to opalescent, colorless to pale brown solution in a single-dose vial for intravenous use. VEGZELMA contains bevacizumab-adcd at a concentration of 25 mg/mL in either 100 mg/4 mL or 400 mg/16 mL single-dose vials.

Each mL of solution contains 25 mg bevacizumab-adcd, dibasic sodium phosphate (1.2 mg), monobasic sodium phosphate (5 mg), polysorbate 20 (0.4 mg), trehalose (54.3 mg), and Water for Injection, USP. The pH is 6.2.

12 CLINICAL PHARMACOLOGY

12.1 Mechanism of Action

Bevacizumab products bind VEGF and prevent the interaction of VEGF to its receptors (Flt-1 and KDR) on the surface of endothelial cells. The interaction of VEGF with its receptors leads to endothelial cell proliferation and new blood vessel formation in in vitro models of angiogenesis. Administration of bevacizumab to xenotransplant models of colon cancer in nude (athymic) mice caused reduction of microvascular growth and inhibition of metastatic disease progression.

12.2 Pharmacokinetics

The pharmacokinetic profile of bevacizumab was assessed using an assay that measures total serum bevacizumab concentrations (i.e., the assay did not distinguish between free bevacizumab and bevacizumab bound to VEGF ligand). Based on a population pharmacokinetic analysis of 491 patients who received 1 to 20 mg/kg of bevacizumab every week, every 2 weeks, or every 3 weeks, bevacizumab pharmacokinetics are linear and the predicted time to reach more than 90% of steady state concentration is 84 days. The accumulation ratio following a dose of 10 mg/kg of bevacizumab once every 2 weeks is 2.8.

Population simulations of bevacizumab exposures provide a median trough concentration of 80.3 mcg/mL on Day 84 (10th, 90th percentile: 45, 128) following a dose of 5 mg/kg once every two weeks.

Distribution

The mean (% coefficient of variation [CV%]) central volume of distribution is 2.9 (22%) L.

Elimination

The mean (CV%) clearance is 0.23 (33) L/day. The estimated half-life is 20 days (11 to 50 days).

Specific Populations

The clearance of bevacizumab varied by body weight, sex, and tumor burden. After correcting for body weight, males had a higher bevacizumab clearance (0.26 L/day vs. 0.21 L/day) and a larger central volume of distribution (3.2 L vs. 2.7 L) than females. Patients with higher tumor burden (at or above median value of tumor surface area) had a higher bevacizumab clearance (0.25 L/day vs. 0.20 L/day) than patients with tumor burdens below the median. In Study AVF2107g, there was no evidence of lesser efficacy (hazard ratio for overall survival) in males or patients with higher tumor burden treated with bevacizumab as compared to females and patients with low tumor burden.

13 NONCLINICAL TOXICOLOGY

13.1 Carcinogenesis, Mutagenesis, Impairment of Fertility

No studies have been conducted to assess potential of bevacizumab products for carcinogenicity or mutagenicity.

Bevacizumab products may impair fertility. Female cynomolgus monkeys treated with 0.4 to 20 times the recommended human dose of bevacizumab exhibited arrested follicular development or absent corpora lutea, as well as dose-related decreases in ovarian and uterine weights, endometrial proliferation, and the number of menstrual cycles. Following a 4- or 12-week recovery period, there was a trend suggestive of reversibility. After the 12-week recovery period, follicular maturation arrest was no longer observed, but ovarian weights were still moderately decreased. Reduced endometrial proliferation was no longer observed at the 12-week recovery time point; however, decreased uterine weight, absent corpora lutea, and reduced number of menstrual cycles remained evident.

13.2 Animal Toxicology and/or Pharmacology

Rabbits dosed with bevacizumab exhibited reduced wound healing capacity. Using full-thickness skin incision and partial thickness circular dermal wound models, bevacizumab dosing resulted in reductions in wound tensile strength, decreased granulation and re-epithelialization, and delayed time to wound closure.

14 CLINICAL STUDIES

14.1 Metastatic Colorectal Cancer

Study AVF2107g

The safety and efficacy of bevacizumab was evaluated in a double-blind, active-controlled study [AVF2107g (NCT00109070)] in 923 patients with previously untreated mCRC who were randomized (1:1:1) to placebo with bolus-IFL (irinotecan 125 mg/m^2, fluorouracil 500 mg/m^2, and leucovorin 20 mg/m^2 given once weekly for 4 weeks every 6 weeks), bevacizumab (5 mg/kg every 2 weeks) with bolus-IFL, or bevacizumab (5 mg/kg every 2 weeks) with fluorouracil and leucovorin. Enrollment to the bevacizumab with fluorouracil and leucovorin arm was discontinued, after enrollment of 110 patients in accordance with the protocol-specified adaptive design. Bevacizumab was continued until disease progression or unacceptable toxicity or for a maximum of 96 weeks. The main outcome measure was overall survival (OS).

The median age was 60 years; 60% were male, 79% were White, 57% had an ECOG performance status of 0, 21% had a rectal primary and 28% received prior adjuvant chemotherapy. The dominant site of disease was extra-abdominal in 56% of patients and was the liver in 38% of patients.

The addition of bevacizumab improved survival across subgroups defined by age (<65 years, ≥ 65 years) and sex. Results are presented in Table 9 and Figure 1.

Table 9: Efficacy Results in Study AVF2107g
Efficacy Parameter | Bevacizumab with bolus-IFL (N=402) | Placebo with bolus-IFL (N=411)
Overall Survival
Median, in months | 20.3 | 15.6
Hazard ratio (95% CI) | 0.66 (0.54, 0.81)
p-value [by stratified log-rank test.] | < 0.001
Progression-Free Survival
Median, in months | 10.6 | 6.2
Hazard ratio (95% CI) | 0.54 (0.45, 0.66)
p-value | < 0.001
Overall Response Rate
Rate (%) | 45% | 35%
p-value [by χ2 test] | < 0.01
Duration of Response
Median, in months | 10.4 | 7.1

Figure 1: Kaplan-Meier Curves for Duration of Survival in Metastatic Colorectal Cancer in Study AVF2107g

Among the 110 patients randomized to bevacizumab with fluorouracil and leucovorin, median OS was 18.3 months, median progression-free survival (PFS) was 8.8 months, overall response rate (ORR) was 39%, and median duration of response was 8.5 months.

Study E3200

The safety and efficacy of bevacizumab were evaluated in a randomized, open-label, active-controlled study [E3200 (NCT00025337)] in 829 patients who were previously treated with irinotecan and fluorouracil for initial therapy for metastatic disease or as adjuvant therapy. Patients were randomized (1:1:1) to FOLFOX4 (Day 1: oxaliplatin 85 mg/m^2 and leucovorin 200 mg/m^2 concurrently, then fluorouracil 400 mg/m^2 bolus followed by 600 mg/m^2 continuously; Day 2: leucovorin 200 mg/m^2, then fluorouracil 400 mg/m^2 bolus followed by 600 mg/m^2 continuously; every 2 weeks), bevacizumab (10 mg/kg every 2 weeks prior to FOLFOX4 on Day 1) with FOLFOX4, or bevacizumab alone (10 mg/kg every 2 weeks). Bevacizumab was continued until disease progression or unacceptable toxicity. The main outcome measure was OS.

The bevacizumab alone arm was closed to accrual after enrollment of 244 of the planned 290 patients following a planned interim analysis by the data monitoring committee based on evidence of decreased survival compared to FOLFOX4 alone.

The median age was 61 years; 60% were male, 87% were White, 49% had an ECOG performance status of 0, 26% received prior radiation therapy, and 80% received prior adjuvant chemotherapy, 99% received prior irinotecan with or without fluorouracil for metastatic disease, and 1% received prior irinotecan and fluorouracil as adjuvant therapy.

The addition of bevacizumab to FOLFOX4 resulted in significantly longer survival as compared to FOLFOX4 alone; median OS was 13.0 months vs. 10.8 months [hazard ratio (HR) 0.75 (95% CI: 0.63, 0.89), p-value of 0.001 stratified log-rank test] with clinical benefit seen in subgroups defined by age (<65 years, ≥ 65 years) and sex. PFS and ORR based on investigator assessment were higher in patients receiving bevacizumab with FOLFOX4.

Study TRC-0301

The activity of bevacizumab with fluorouracil (as bolus or infusion) and leucovorin was evaluated in a single arm study [TRC-0301 (NCT00066846)] enrolling 339 patients with mCRC with disease progression following both irinotecan- and oxaliplatin-based chemotherapy. Seventy-three percent of patients received concurrent bolus fluorouracil and leucovorin. One objective partial response was verified in the first 100 evaluable patients for an ORR of 1% (95% CI: 0%, 5.5%).

Study ML18147

The safety and efficacy of bevacizumab were evaluated in a prospective, randomized, open-label, multinational, controlled study [ML18147 (NCT00700102)] in 820 patients with histologically confirmed mCRC who had progressed on a first-line bevacizumab-containing regimen. Patients were excluded if they progressed within 3 months of initiating first-line chemotherapy and if they received bevacizumab for less than 3 consecutive months in the first-line setting. Patients were randomized (1:1) within 3 months after discontinuing bevacizumab as first-line treatment to receive fluoropyrimidine-irinotecan- or fluoropyrimidine-oxaliplatin-based chemotherapy with or without bevacizumab (5 mg/kg every 2 weeks or 7.5 mg/kg every 3 weeks). The choice of second-line treatment was contingent upon first-line chemotherapy. Second-line treatment was administered until progressive disease or unacceptable toxicity. The main outcome measure was OS. A secondary outcome measure was ORR.

The median age was 63 years (21 to 84 years); 64% were male, 52% had an ECOG performance status of 1, 44% had an ECOG performance status of 0, 58% received irinotecan-based therapy as first-line treatment, 55% progressed on first-line treatment within 9 months, and 77% received their last dose of bevacizumab as first-line treatment within 42 days of being randomized. Second-line chemotherapy regimens were generally balanced between each arm.

The addition of bevacizumab to fluoropyrimidine-based chemotherapy resulted in a statistically significant prolongation of OS and PFS. There was no significant difference in ORR. Results are presented in Table 10 and Figure 2.

Table 10: Efficacy Results in Study ML18147
Efficacy Parameter | Bevacizumab with Chemotherapy (N=409) | Chemotherapy (N=411)
Overall Survival [p = 0.0057 by unstratified log-rank test.]
Median, in months | 11.2 | 9.8
Hazard ratio (95% CI) | 0.81 (0.69, 0.94)
Progression-Free Survival [p-value < 0.0001 by unstratified log-rank test.]
Median, in months | 5.7 | 4.0
Hazard ratio (95% CI) | 0.68 (0.59, 0.78)

Figure 2: Kaplan-Meier Curves for Duration of Survival in Metastatic Colorectal Cancer in Study ML18147

14.2 Lack of Efficacy in Adjuvant Treatment of Colon Cancer

Lack of efficacy of bevacizumab as an adjunct to standard chemotherapy for the adjuvant treatment of colon cancer was determined in two randomized, open-label, multicenter clinical studies.

The first study [BO17920 (NCT00112918)] was conducted in 3451 patients with high-risk stage II and III colon cancer, who had undergone surgery for colon cancer with curative intent. Patients were randomized to receive bevacizumab at a dose equivalent to 2.5 mg/kg/week on either a 2-weekly schedule with FOLFOX4 (N=1155) or on a 3-weekly schedule with XELOX (N=1145) or FOLFOX4 alone (N=1151). The main outcome measure was disease free survival (DFS) in patients with stage III colon cancer.

The median age was 58 years; 54% were male, 84% were White and 29% were ≥ 65 years. Eighty-three percent had stage III disease.

The addition of bevacizumab to chemotherapy did not improve DFS. As compared to FOLFOX4 alone, the proportion of stage III patients with disease recurrence or with death due to disease progression were numerically higher for patients receiving bevacizumab with FOLFOX4 or with XELOX. The hazard ratios for DFS were 1.17 (95% CI: 0.98,1.39) for bevacizumab with FOLFOX4 versus FOLFOX4 alone and 1.07 (95% CI: 0.90, 1.28) for bevacizumab with XELOX versus FOLFOX4 alone. The hazard ratios for OS were 1.31 (95% CI: 1.03, 1.67) and 1.27 (95% CI: 1, 1.62) for the comparison of bevacizumab with FOLFOX4 versus FOLFOX4 alone and bevacizumab with XELOX versus FOLFOX4 alone, respectively. Similar lack of efficacy for DFS was observed in the bevacizumab-containing arms compared to FOLFOX4 alone in the high-risk stage II cohort.

In a second study [NSABP-C-08 (NCT00096278)], patients with stage II and III colon cancer who had undergone surgery with curative intent, were randomized to receive either bevacizumab administered at a dose equivalent to 2.5 mg/kg/week with mFOLFOX6 (N=1354) or mFOLFOX6 alone (N=1356). The median age was 57 years, 50% were male and 87% White. Seventy-five percent had stage III disease. The main outcome was DFS among stage III patients. The HR for DFS was 0.92 (95% CI: 0.77, 1.10). OS was not significantly improved with the addition of bevacizumab to mFOLFOX6 [HR 0.96 (95% CI: 0.75, 1.22)].

14.3 First-Line Non–Squamous Non–Small Cell Lung Cancer

Study E4599

The safety and efficacy of bevacizumab as first-line treatment of patients with locally advanced, metastatic, or recurrent non-squamous NSCLC was studied in a single, large, randomized, active-controlled, open-label, multicenter study [E4599 (NCT00021060)]. A total of 878 chemotherapy-naïve patients with locally advanced, metastatic or recurrent non–squamous NSCLC were randomized (1:1) to receive six 21-day cycles of paclitaxel (200 mg/m^2) and carboplatin (AUC 6) with or without bevacizumab 15 mg/kg. After completing or discontinuing chemotherapy, patients randomized to receive bevacizumab continued to receive bevacizumab alone until disease progression or until unacceptable toxicity. The trial excluded patients with predominant squamous histology (mixed cell type tumors only), CNS metastasis, gross hemoptysis (1/2 teaspoon or more of red blood), unstable angina, or receiving therapeutic anticoagulation. The main outcome measure was duration of survival.

The median age was 63 years; 54% were male, 43% were ≥ 65 years, and 28% had ≥5% weight loss at study entry. Eleven percent had recurrent disease. Of the 89% with newly diagnosed NSCLC, 12% had Stage IIIB with malignant pleural effusion and 76% had Stage IV disease.

OS was statistically significantly longer for patients receiving bevacizumab with paclitaxel and carboplatin compared with those receiving chemotherapy alone. Median OS was 12.3 months vs. 10.3 months [HR 0.80 (95% CI: 0.68, 0.94), final p-value of 0.013, stratified log-rank test]. Based on investigator assessment which was not independently verified, patients were reported to have longer PFS with bevacizumab with paclitaxel and carboplatin compared to chemotherapy alone. Results are presented in Figure 3.

Figure 3: Kaplan-Meier Curves for Duration of Survival in First-Line Non-Squamous Non-Small Cell Lung Cancer in Study E4599

In an exploratory analysis across patient subgroups, the impact of bevacizumab on OS was less robust in the following subgroups: women [HR 0.99 (95% CI: 0.79, 1.25)], patients ≥65 years [HR 0.91 (95% CI: 0.72, 1.14)] and patients with ≥5% weight loss at study entry [HR 0.96 (95% CI: 0.73, 1.26)].

Study BO17704

The safety and efficacy of bevacizumab in patients with locally advanced, metastatic or recurrent non-squamous NSCLC, who had not received prior chemotherapy was studied in another randomized, double-blind, placebo-controlled study [BO17704 (NCT00806923)]. A total of 1043 patients were randomized (1:1:1) to receive cisplatin and gemcitabine with placebo, bevacizumab 7.5 mg/kg or bevacizumab 15 mg/kg. The main outcome measure was PFS. Secondary outcome measure was OS.

The median age was 58 years; 36% were female and 29% were ≥ 65 years. Eight percent had recurrent disease and 77% had Stage IV disease.

PFS was significantly higher in both bevacizumab-containing arms compared to the placebo arm [HR 0.75 (95% CI: 0.62, 0.91), p-value of 0.0026 for bevacizumab 7.5 mg/kg and HR 0.82 (95% CI: 0.68, 0.98), p-value of 0.0301 for bevacizumab 15 mg/kg]. The addition of bevacizumab to cisplatin and gemcitabine failed to demonstrate an improvement in the duration of OS [HR 0.93 (95% CI: 0.78, 1.11), p-value of 0.420 for bevacizumab 7.5 mg/kg and HR 1.03 (95% CI: 0.86, 1.23), p-value of 0.761 for bevacizumab 15 mg/kg].

14.4 Recurrent Glioblastoma

Study EORTC 26101

The safety and efficacy of bevacizumab were evaluated in a multicenter, randomized (2:1), open-label study in patients with recurrent GBM (EORTC 26101, NCT01290939). Patients with first progression following radiotherapy and temozolomide were randomized (2:1) to receive bevacizumab (10 mg/kg every 2 weeks) with lomustine (90 mg/m^2 every 6 weeks) or lomustine (110 mg/m^2 every 6 weeks) alone until disease progression or unacceptable toxicity. Randomization was stratified by World Health Organization performance status (0 vs. >0), steroid use (yes vs. no), largest tumor diameter (≤40 vs. >40 mm), and institution. The main outcome measure was OS. Secondary outcome measures were investigator-assessed PFS and ORR per the modified Response Assessment in Neuro-oncology (RANO) criteria, health related quality of life (HRQoL), cognitive function, and corticosteroid use.

A total of 432 patients were randomized to receive lomustine alone (N=149) or bevacizumab with lomustine (N=283). The median age was 57 years; 24.8% of patients were ≥ 65 years. The majority of patients with were male (61%); 66% had a WHO performance status score > 0; and in 56% the largest tumor diameter was ≤ 40 mm. Approximately 33% of patients randomized to receive lomustine received bevacizumab following documented progression.

No difference in OS (HR 0.91, p-value of 0.4578) was observed between arms; therefore, all secondary outcome measures are descriptive only. PFS was longer in the bevacizumab with lomustine arm [HR 0.52 (95% CI: 0.41, 0.64)] with a median PFS of 4.2 months in the bevacizumab with lomustine arm and 1.5 months in the lomustine arm. Among the 50% of patients receiving corticosteroids at the time of randomization, a higher percentage of patients in the bevacizumab with lomustine arm discontinued corticosteroids (23% vs. 12%).

Study AVF3708g and Study NCI 06-C-0064E

The efficacy and safety of bevacizumab 10 mg/kg every 2 weeks in patients with previously treated GBM were evaluated in one single arm single center study (NCI 06-C-0064E) and a randomized noncomparative multicenter study [AVF3708g (NCT00345163)]. Response rates in both studies were evaluated based on modified WHO criteria that considered corticosteroid use. In AVF3708g, the response rate was 25.9% (95% CI: 17%, 36.1%) with a median duration of response of 4.2 months (95% CI: 3, 5.7). In Study NCI 06-C-0064E, the response rate was 19.6% (95% CI: 10.9%, 31.3%) with a median duration of response of 3.9 months (95% CI: 2.4, 17.4).

14.5 Metastatic Renal Cell Carcinoma

Study BO17705

The safety and efficacy of bevacizumab were evaluated in patients with treatment-naïve mRCC in a multicenter, randomized, double-blind, international study [BO17705 (NCT00738530)] comparing interferon alfa and bevacizumab versus interferon alfa and placebo. A total of 649 patients who had undergone a nephrectomy were randomized (1:1) to receive either bevacizumab (10 mg/kg every 2 weeks; N=327) or placebo (every 2 weeks; N=322) with interferon alfa (9 MIU subcutaneously three times weekly for a maximum of 52 weeks). Patients were treated until disease progression or unacceptable toxicity. The main outcome measure was investigator-assessed PFS. Secondary outcome measures were ORR and OS.

The median age was 60 years (18 to 82 years); 70% were male and 96% were White. The study population was characterized by Motzer scores as follows: 28% favorable (0), 56% intermediate (1–2), 8% poor (3–5), and 7% missing.

PFS was statistically significantly prolonged among patients receiving bevacizumab compared to placebo; median PFS was 10.2 months vs. 5.4 months [HR 0.60 (95% CI: 0.49, 0.72), p-value < 0.0001, stratified log-rank test]. Among the 595 patients with measurable disease, ORR was also significantly higher (30% vs. 12%, p-value < 0.0001, stratified CMH test). There was no improvement in OS based on the final analysis conducted after 444 deaths, with a median OS of 23 months in the patients receiving bevacizumab with interferon alfa and 21 months in patients receiving interferon alone [HR 0.86, (95% CI: 0.72, 1.04)]. Results are presented in Figure 4.

Figure 4: Kaplan-Meier Curves for Progression-Free Survival in Metastatic Renal Cell Carcinoma in Study BO17705

14.6 Persistent, Recurrent, or Metastatic Cervical Cancer

Study GOG-0240

The safety and efficacy of bevacizumab were evaluated in patients with persistent, recurrent, or metastatic cervical cancer in a randomized, four-arm, multicenter study comparing bevacizumab with chemotherapy versus chemotherapy alone [GOG-0240 (NCT00803062)]. A total of 452 patients were randomized (1:1:1:1) to receive paclitaxel and cisplatin with or without bevacizumab, or paclitaxel and topotecan with or without bevacizumab.

The dosing regimens for bevacizumab, paclitaxel, cisplatin and topotecan were as follows:

- Day 1: Paclitaxel 135 mg/m^2 over 24 hours, Day 2: cisplatin 50 mg/m^2 with bevacizumab;
- Day 1: Paclitaxel 175 mg/m^2 over 3 hours, Day 2: cisplatin 50 mg/m^2 with bevacizumab;
- Day 1: Paclitaxel 175 mg/m^2 over 3 hours with cisplatin 50 mg/m^2 with bevacizumab;
- Day 1: Paclitaxel 175 mg/m^2 over 3 hours with bevacizumab, Days 13: topotecan IV 0.75 mg/m^2 over 30 minutes.

Patients were treated until disease progression or unacceptable adverse reactions. The main outcome measure was OS. Secondary outcome measures included ORR.

The median age was 48 years (20 to 85 years). Of the 452 patients randomized at baseline, 78% of patients were White, 80% had received prior radiation, 74% had received prior chemotherapy concurrent with radiation, and 32% had a platinum-free interval (PFI) of less than 6 months. Patients had a GOG performance status of 0 (58%) or 1 (42%). Demographic and disease characteristics were balanced across arms.

Results are presented in Figure 5 and Table 11.

Figure 5: Kaplan-Meier Curves for Overall Survival in Persistent, Recurrent, or Metastatic Cervical Cancer in Study GOG-0240

Table 11: Efficacy Results in Study GOG-0240
Efficacy Parameter | Bevacizumab with Chemotherapy (N=227) | Chemotherapy (N=225)
Overall Survival
Median, in months [Kaplan-Meier estimates.] | 16.8 | 12.9
Hazard ratio (95% CI) | 0.74 (0.58; 0.94)
p-value [log-rank test (stratified).] | 0.0132

The ORR was higher in patients who received bevacizumab with chemotherapy [45% (95% CI: 39, 52)] compared to patients who received chemotherapy alone [34% (95% CI: 28,40)].

Table 12: Efficacy Results in Study GOG-0240
Efficacy Parameter | Topotecan and Paclitaxel with or without Bevacizumab (N=223) | Cisplatin and Paclitaxel with or without Bevacizumab (N=229)
Overall Survival
Median, in months [Kaplan-Meier estimates.] | 13.3 | 15.5
Hazard ratio (95% CI) | 1.15 (0.91, 1.46)
p-value | 0.23

The HR for OS with bevacizumab with cisplatin and paclitaxel as compared to cisplatin and paclitaxel alone was 0.72 (95% CI: 0.51, 1.02). The HR for OS with bevacizumab with topotecan and paclitaxel as compared to topotecan and paclitaxel alone was 0.76 (95% CI: 0.55, 1.06).

14.7 Stage III or IV Epithelial Ovarian, Fallopian Tube, or Primary Peritoneal Cancer Following Initial Surgical Resection

Study GOG-0218

The safety and efficacy of bevacizumab were evaluated in a multicenter, randomized, double-blind, placebo controlled, three arm study [Study GOG-0218 (NCT00262847)] evaluating the effect of adding bevacizumab to carboplatin and paclitaxel for the treatment of patients with stage III or IV epithelial ovarian, fallopian tube or primary peritoneal cancer (N=1873) following initial surgical resection. Patients were randomized (1:1:1) to one of the following arms:

- CPP: carboplatin (AUC 6) and paclitaxel (175 mg/m^2) for six cycles, with concurrent placebo started at cycle 2, followed by placebo alone every three weeks for a total of up to 22 cycles of therapy (n=625) or
- CPB15: carboplatin (AUC 6) and paclitaxel (175 mg/m^2) for six cycles, with concurrent bevacizumab started at cycle 2, followed by placebo alone every three weeks for a total of up to 22 cycles of therapy (n=625) or
- CPB15+: carboplatin (AUC 6) and paclitaxel (175 mg/m^2) for six cycles, with concurrent bevacizumab started at cycle 2, followed by bevacizumab as a single agent every three weeks for a total of up to 22 cycles of therapy (n=623).

The main outcome measure was investigator-assessed PFS. OS was a secondary outcome measure.

The median age was 60 years (range 22-89 years) and 28% of patients were >65 years of age. Overall, approximately 50% of patients had a GOG PS of 0 at baseline, and 43% a GOG PS score of 1. Patients had either epithelial ovarian cancer (83%), primary peritoneal cancer (15%), or fallopian tube cancer (2%). Serous adenocarcinoma was the most common histologic type (85% in CPP and CPB15 arms, 86% in CPB15+arm). Overall, approximately 34% of patients had resected FIGO Stage III with residual disease < 1 cm, 40% had resected Stage III with residual disease >1 cm, and 26% had resected Stage IV disease.

The majority of patients in all three treatment arms received subsequent antineoplastic treatment, 78.1% in the CPP arm, 78.6% in the CPB15 arm, and 73.2% in the CPB15+ arm. A higher proportion of patients in the CPP arm (25.3%) and CPB15 arm (26.6%) received at least one anti-angiogenic (including bevacizumab) treatment after discontinuing from study compared with the CPB15+ arm (15.6%).

Study results are presented in Table 13 and Figure 6.

Table 13: Efficacy Results in Study GOG-0218
Efficacy Parameter | Bevacizumab with carboplatin and paclitaxel followed by bevacizumab alone (N=623) | Bevacizumab with carboplatin and paclitaxel (N=625) | Carboplatin and paclitaxel (N=625)
NS=not significant.
Progression-Free Survival per Investigator
Median, in months | 18.2 | 12.8 | 12.0
Hazard ratio (95% CI) [Relative to the control arm; stratified hazard ratio] | 0.62 (0.52, 0.75) | 0.83 (0.70, 0.98)
p-value [Two-sided p-value based on re-randomization test] | < 0.0001 | NS
Overall Survival [Final overall survival analysis]
Median, in months | 43.8 | 38.8 | 40.6
Hazard ratio (95% CI) | 0.89 (0.76, 1.05) | 1.06 (0.90, 1.24)

Figure 6: Kaplan-Meier Curves for Investigator-Assessed Progression-Free Survival in Stage III or IV Epithelial Ovarian, Fallopian Tube, or Primary Peritoneal Cancer Following Initial Surgical Resection in Study GOG-0218

14.8 Platinum-Resistant Recurrent Epithelial Ovarian, Fallopian Tube, or Primary Peritoneal Cancer

Study MO22224

The safety and efficacy of bevacizumab were evaluated in a multicenter, open-label, randomized study [MO22224 (NCT00976911)] comparing bevacizumab with chemotherapy versus chemotherapy alone in patients with platinum-resistant recurrent epithelial ovarian, fallopian tube, or primary peritoneal cancer that recurred within <6 months from the most recent platinum-based therapy (N=361). Patients had received no more than 2 prior chemotherapy regimens. Patients received one of the following chemotherapy regimens at the discretion of the investigator: paclitaxel (80 mg/m^2 on days 1, 8, 15 and 22 every 4 weeks); pegylated liposomal doxorubicin (40 mg/m^2 on day 1 every 4 weeks); or topotecan (4 mg/m^2 on days 1, 8 and 15 every 4 weeks or 1.25 mg/m^2 on days 15 every 3 weeks). Patients were treated until disease progression, unacceptable toxicity, or withdrawal. Forty percent of patients on the chemotherapy alone arm received bevacizumab alone upon progression. The main outcome measure was investigator-assessed PFS. Secondary outcome measures were ORR and OS.

The median age was 61 years (25 to 84 years) and 37% of patients were ≥65 years. Seventy-nine percent had measurable disease at baseline, 87% had baseline CA-125 levels ≥2 times ULN and 31% had ascites at baseline. Seventy-three percent had a PFI of 3 months to 6 months and 27% had PFI of <3 months. ECOG performance status was 0 for 59%, 1 for 34%, and 2 for 7% of the patients.

The addition of bevacizumab to chemotherapy demonstrated a statistically significant improvement in investigator-assessed PFS, which was supported by a retrospective independent review analysis. Results for the ITT population are presented in Table 14 and Figure 7. Results for the separate chemotherapy cohorts are presented in Table 15.

Table 14: Efficacy Results in Study MO22224
Efficacy Parameter | Bevacizumab with Chemotherapy (N=179) | Chemotherapy (N=182)
Progression-Free Survival per Investigator
Median (95% CI), in months | 6.8 (5.6, 7.8) | 3.4 (2.1, 3.8)
HR (95% CI) [per stratified Cox proportional hazards model] | 0.38 (0.30, 0.49)
p-value [per stratified log-rank test] | < 0.0001
Overall Survival
Median (95% CI), in months | 16.6 (13.7, 19.0) | 13.3 (11.9, 16.4)
HR (95% CI) | 0.89 (0.69, 1.14)
Overall Response Rate
Number of patients with measurable disease at baseline | 142 | 144
Rate, % (95% CI) | 28% (21%, 36%) | 13% (7%, 18%)
Duration of Response
Median, in months | 9.4 | 5.4

Figure 7: Kaplan-Meier Curves for Investigator-Assessed Progression-Free Survival in Platinum-Resistant Recurrent Epithelial Ovarian, Fallopian Tube, or Primary Peritoneal Cancer in Study MO22224

Table 15: Efficacy Results in Study MO22224 by Chemotherapy
Efficacy Parameter | Paclitaxel |  | Topotecan |  | Pegylated Liposomal Doxorubicin
Efficacy Parameter | Bevacizumab with Chemotherapy | Chemotherapy | Bevacizumab with Chemotherapy | Chemotherapy | Bevacizumab with Chemotherapy | Chemotherapy
Efficacy Parameter | (N=60) | (N=55) | (N=57) | (N=63) | (N=62) | (N=64)
NE=Not Estimable.
Progression-Free Survival per Investigator
Median, in months (95% CI) | 9.6 (7.8, 11.5) | 3.9 (3.5, 5.5) | 6.2 (5.3, 7.6) | 2.1 (1.9, 2.3) | 5.1 (3.9, 6.3) | 3.5 (1.9, 3.9)
Hazard ratio [per stratified Cox proportional hazards model.] (95% CI) | 0.47 (0.31, 0.72) |  | 0.24 (0.15, 0.38) |  | 0.47 (0.32, 0.71)
Overall Survival
Median, in months (95% CI) | 22.4 (16.7, 26.7) | 13.2 (8.2, 19.7) | 13.8 (11.0, 18.3) | 13.3 (10.4, 18.3) | 13.7 (11.0, 18.3) | 14.1 (9.9, 17.8)
Hazard ratio (95% CI) | 0.64 (0.41, 1.01) |  | 1.12 (0.73, 1.73) |  | 0.94 (0.63, 1.42)
Overall Response Rate
Number of patients with measurable disease at baseline | 45 | 43 | 46 | 50 | 51 | 51
Rate, % (95% CI) | 53 (39, 68) | 30 (17, 44) | 17 (6, 28) | 2 (0, 6) | 16 (6, 26) | 8 (0, 15)
Duration of Response
Median, in months | 11.6 | 6.8 | 5.2 | NE | 8.0 | 4.6

14.9 Platinum-Sensitive Recurrent Epithelial Ovarian, Fallopian Tube, or Primary Peritoneal Cancer

Study AVF4095g

The safety and efficacy of bevacizumab were evaluated in a randomized, double-blind, placebo-controlled study [AVF4095g (NCT00434642)] studying bevacizumab with chemotherapy versus chemotherapy alone in the treatment of patients with platinum-sensitive recurrent epithelial ovarian, fallopian tube, or primary peritoneal cancer who have not received prior chemotherapy in the recurrent setting or prior bevacizumab treatment (N=484). Patients were randomized (1:1) to receive bevacizumab (15 mg/kg day 1) or placebo every 3 weeks with carboplatin (AUC 4, day 1) and gemcitabine (1000 mg/m^2 on days 1 and 8) a for 6 to 10 cycles followed by bevacizumab or placebo alone until disease progression or unacceptable toxicity. The main outcome measures were investigator-assessed PFS. Secondary outcome measures were ORR and OS.

The median age was 61 years (28 to 87 years) and 37% of patients were ≥65 years. All patients had measurable disease at baseline, 74% had baseline CA-125 levels >ULN (35 U/mL). The platinum-free interval (PFI) was 6 months to 12 months in 42 % of patients and >12 months in 58% of patients. The ECOG performance status was 0 or 1 for 99.8% of patients.

A statistically significant prolongation in PFS was demonstrated among patients receiving bevacizumab with chemotherapy compared to those receiving placebo with chemotherapy (Table 18 and Figure 8). Independent radiology review of PFS was consistent with investigator assessment [HR 0.45 (95% CI: 0.35, 0.58)]. OS was not significantly improved with the addition of Avastin to chemotherapy [HR 0.95 (95% CI: 0.77, 1.17)].

Table 16: Efficacy Results in Study AVF4095g
Efficacy Parameter | Bevacizumab with Gemcitabine and Carboplatin (N=242) | Placebo with Gemcitabine and Carboplatin (N=242)
Progression-Free Survival
Median, in months | 12.4 | 8.4
Hazard ratio (95% CI) | 0.46 (0.37, 0.58)
p-value | < 0.0001
Overall Response Rate
% patients with overall response | 78% | 57%
p-value | < 0.0001

Figure 8: Kaplan-Meier Curves for Progression-Free Survival in Platinum-Sensitive Recurrent Epithelial Ovarian, Fallopian Tube, or Primary Peritoneal Cancer in Study AVF4095g

Study GOG-0213

The safety and efficacy of bevacizumab were evaluated in a randomized, controlled, open-label study [Study GOG-0213 (NCT00565851)] of bevacizumab with chemotherapy versus chemotherapy alone in the treatment of patients with platinum-sensitive recurrent epithelial ovarian, fallopian tube, or primary peritoneal cancer, who have not received more than one previous regimen of chemotherapy (N=673). Patients were randomized (1:1) to receive carboplatin (AUC 5) and paclitaxel (175 mg/m^2 IV over 3 hours) every 3 weeks for 6 to 8 cycles (N=336) or bevacizumab (15 mg/kg) every 3 weeks with carboplatin (AUC 5) and paclitaxel (175 mg/m^2 IV over 3 hours) for 6 to 8 cycles followed by bevacizumab (15 mg/kg every 3 weeks) as a single agent until disease progression or unacceptable toxicity. The main outcome measure was OS. Other outcome measures were investigator-assessed PFS, and ORR.

The median age was 60 years (23 to 85 years) and 33% of patients were 65 years. Eighty-three percent had measurable disease at baseline and 74% had abnormal CA-125 levels at baseline. Ten percent of patients had received prior bevacizumab. Twenty-six percent had a PFI of 6 months to 12 months and 74% had a PFI of >12 months. GOG performance status was 0 or 1 for 99% of patients.

Results are presented in Table 17 and Figure 9.

Table 17: Efficacy Results in Study GOG-0213
Efficacy Parameter | Bevacizumab with Carboplatin and Paclitaxel (N=337) | Carboplatin and Paclitaxel (N=336)
Overall Survival
Median, in months | 42.6 | 37.3
Hazard ratio (95% CI) (IVRS) [HR was estimated from Cox proportional hazards models stratified by the duration of treatment free-interval prior to enrolling onto this study per IVRS (interactive voice response system) and secondary surgical debulking status.] | 0.84 (0.69, 1.01)
Hazard ratio (95% CI) (eCRF) [HR was estimated from Cox proportional hazards models stratified by the duration of platinum free-interval prior to enrolling onto this study per eCRF (electronic case report form) and secondary surgical debulking status.] | 0.82 (0.68, 0.996)
Progression-Free Survival
Median, in months | 13.8 | 10.4
Hazard ratio (95% CI) (IVRS) | 0.61 (0.51, 0.72)
Overall Response Rate
Number of patients with measurable; disease at baseline | 274 | 286
Rate, % | 213 (78%) | 159 (56%)

Figure 9: Kaplan-Meier Curves for Overall Survival in Platinum-Sensitive Recurrent Epithelial Ovarian, Fallopian Tube, or Primary Peritoneal Cancer in Study GOG-0213

16 HOW SUPPLIED/STORAGE AND HANDLING

VEGZELMA (bevacizumab-adcd) injection is a clear to opalescent, colorless to pale brown, sterile solution for intravenous infusion supplied in a single-dose vial pakcaged within cartons in the following strengths and packaging configurations:

- 100 mg/4 mL (25 mg/mL): carton of one vial (NDC 72606-011-01); carton of 10 vials (NDC 72606-011-10).
- 400 mg/16 mL (25 mg/mL): carton of one vial (NDC 72606-012-01); carton of 10 vials (NDC 72606-012-10).

STORAGE AND HANDLING

Store refrigerated at 2°C to 8°C (36°F to 46°F) in the original carton until time of use to protect from light. Do not freeze or shake the vial or carton.

17 PATIENT COUNSELING INFORMATION

Gastrointestinal Perforations and Fistulae

Bevacizumab products may increase the risk of developing gastrointestinal perforations and fistulae. Advise patients to immediately contact their health care provider for high fever, rigors, persistent or severe abdominal pain, severe constipation, or vomiting [see Warnings and Precautions (5.1)].

Surgery and Wound Healing Complications

Bevacizumab products can increase the risk of wound healing complications. Instruct patients not to undergo surgery without first discussing this potential risk with their health care provider [see Warnings and Precautions (5.2)].

Hemorrhage

Bevacizumab products can increase the risk of hemorrhage. Advise patients to immediately contact their health care provider for signs and symptoms of serious or unusual bleeding including coughing or spitting blood [see Warnings and Precautions (5.3)].

Arterial and Venous Thromboembolic Events

Bevacizumab products increase the risk of arterial and venous thromboembolic events. Advise patients to immediately contact their health care provider for signs and symptoms of arterial or venous thromboembolism [see Warnings and Precautions (5.4, 5.5)].

Hypertension

Bevacizumab products can increase blood pressure. Advise patients that they will undergo routine blood pressure monitoring and to contact their health care provider if they experience changes in blood pressure [see Warnings and Precautions (5.6)].

Posterior Reversible Leukoencephalopathy Syndrome

Posterior reversible encephalopathy syndrome (PRES) has been associated with bevacizumab products treatment. Advise patients to immediately contact their health care provider for new onset or worsening neurological function [see Warnings and Precautions (5.7)].

Renal Injury and Proteinuria

Bevacizumab products increase the risk of proteinuria and renal injury, including nephrotic syndrome. Advise patients that treatment with VEGZELMA requires regular monitoring of renal function and to contact their health care provider for proteinuria or signs and symptoms of nephrotic syndrome [see Warnings and Precautions (5.8)].

Infusion-Related Reactions

Bevacizumab products can cause infusion-related reactions. Advise patients to contact their health care provider immediately for signs or symptoms of infusion-related reactions [see Warnings and Precautions (5.9)].

Congestive Heart Failure

Bevacizumab products can increase the risk of developing congestive heart failure. Advise patients to contact their health care provider immediately for signs and symptoms of CHF [see Warnings and Precautions (5.12)].

Embryo-Fetal Toxicity

Advise female patients that bevacizumab products may cause fetal harm and to inform their health care provider with a known or suspected pregnancy [see Warnings and Precautions (5.10), Use in Specific Populations (8.1)]. Advise females of reproductive potential to use effective contraception during treatment with VEGZELMA and for 6 months after the last dose of VEGZELMA [see Use in Specific Populations (8.3)].

Ovarian Failure

Bevacizumab products may lead to ovarian failure. Advise patients of potential options for preservation of ova prior to starting treatment [see Warnings and Precautions (5.11)].

Lactation

Advise women not to breastfeed during treatment with VEGZELMA and for 6 months after the last dose [see Use in Specific Populations (8.2)].

Vegzelma®
(bevacizumab-adcd) Manufactured by
CELLTRION, Inc. 20, Academy-ro
Yeonsu-gu, Incheon
22014, Republic of Korea US License No.: 1996

Distributed by CELLTRION USA, Inc.

1 Evertrust Plaza Suite 1207 Jersey City, NJ 07302

PRINCIPAL DISPLAY PANEL - 4 mL Vial Carton

NDC 72606-011-01
Rx only Vegzelma®
(bevacizumab–adcd) Injection
100 mg/4 mL
(25 mg/mL)

For Intravenous Use.
Single-Dose Vial.
Discard Unused Portion.

1 vial
CELLTRION USA, Inc.

PRINCIPAL DISPLAY PANEL - 16 mL Vial Carton

NDC 72606-012-01

Vegzelma®
(bevacizumab–adcd)

Injection
400 mg/16 mL
(25 mg/mL)

For Intravenous Use.
Single-Dose Vial.
Discard Unused Portion.

1 vial
CELLTRION USA, Inc.